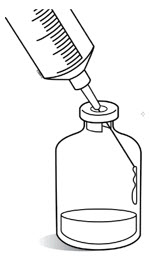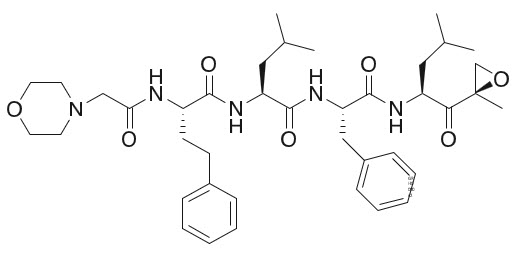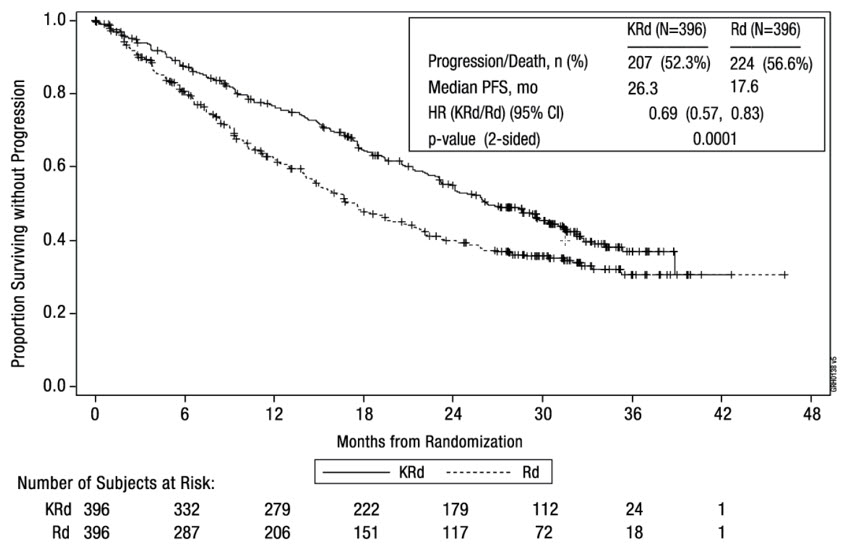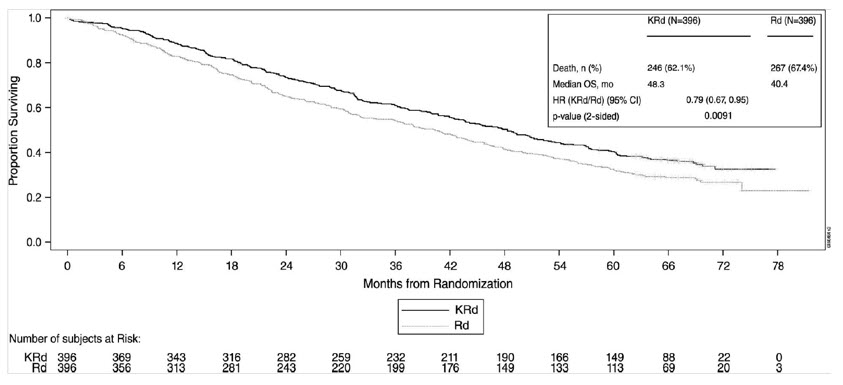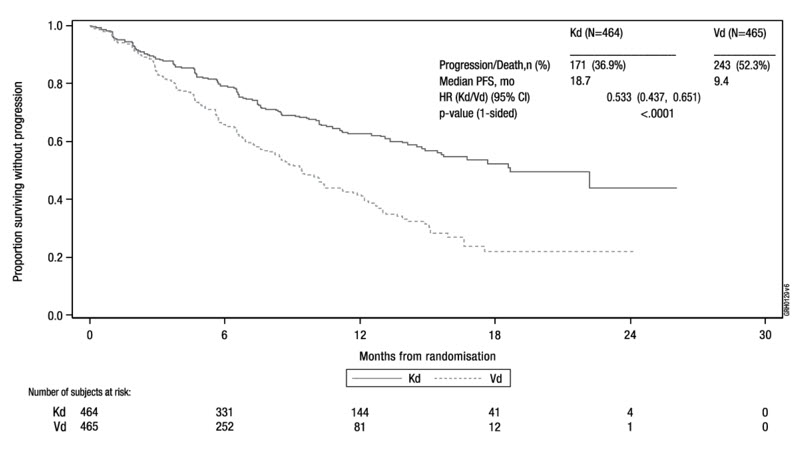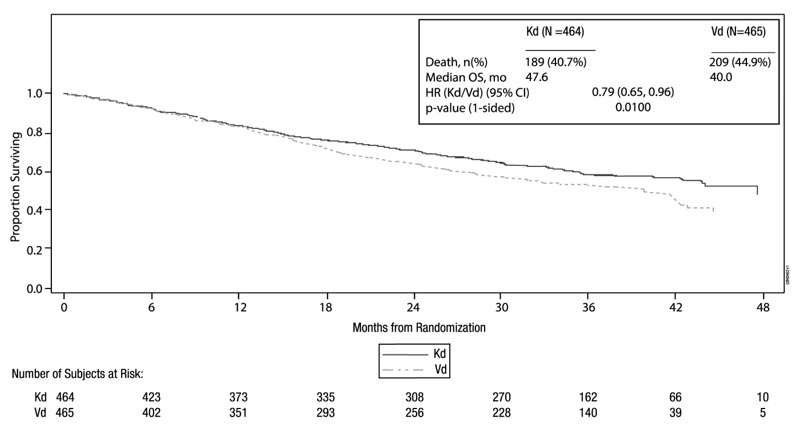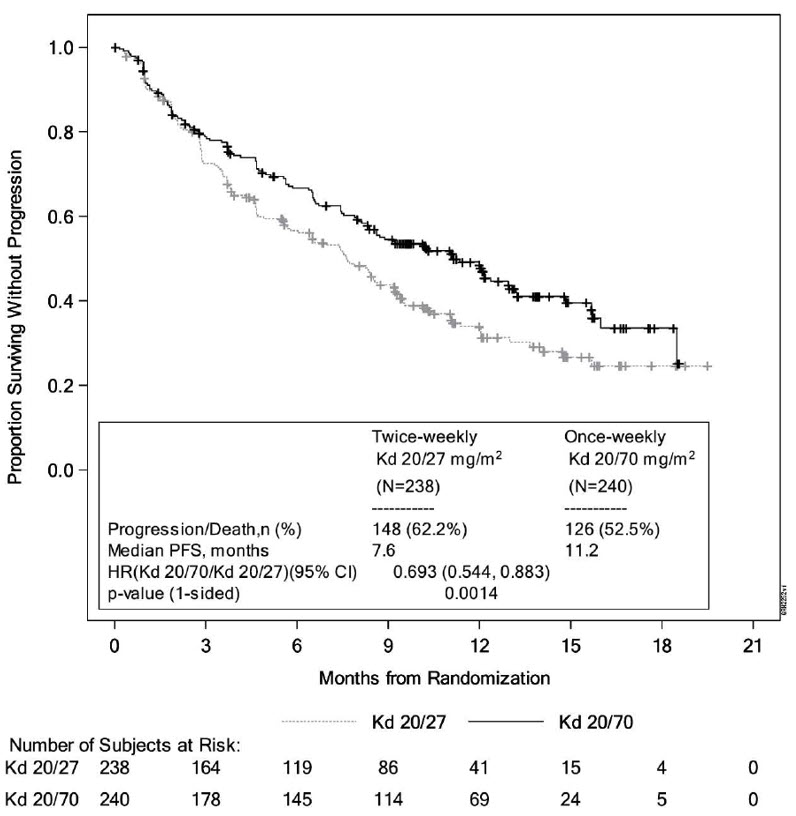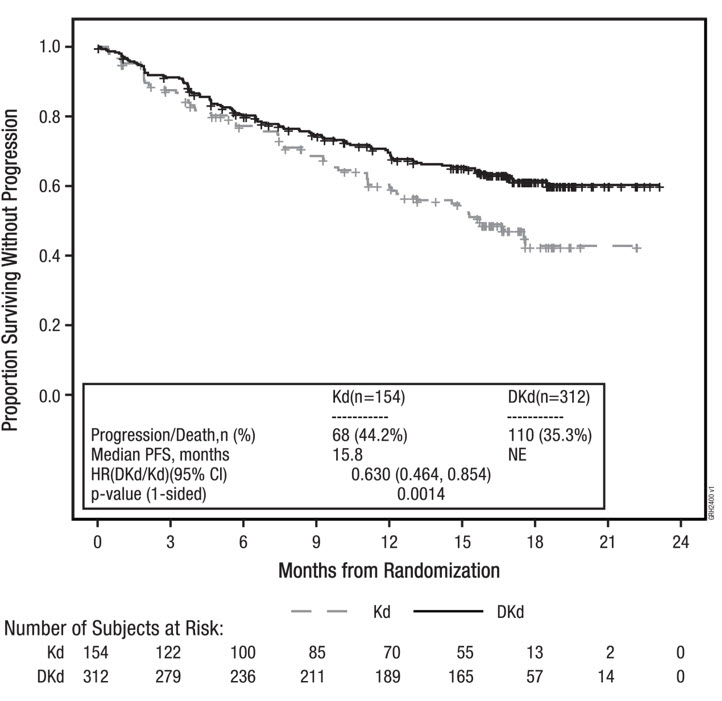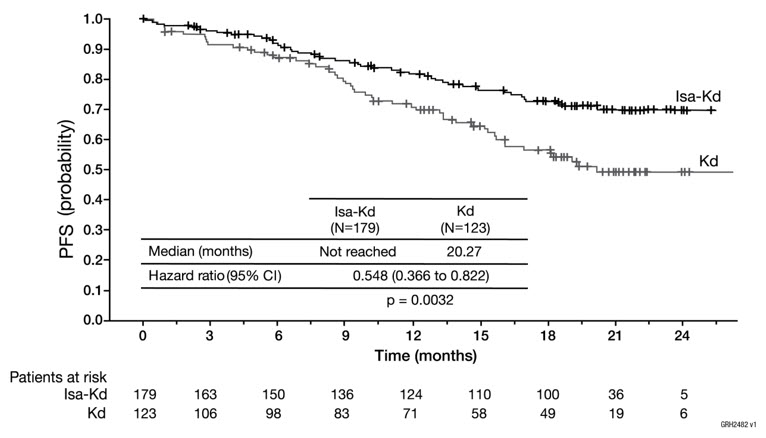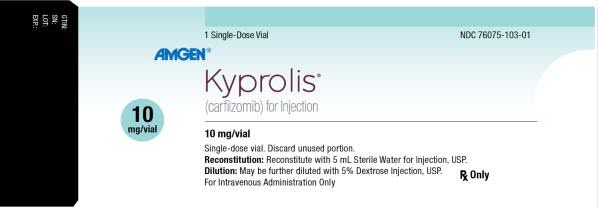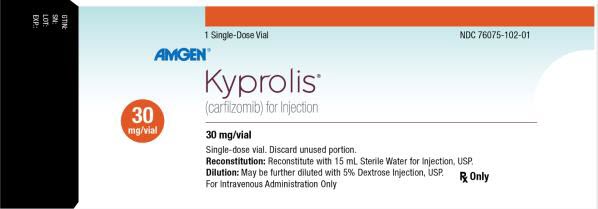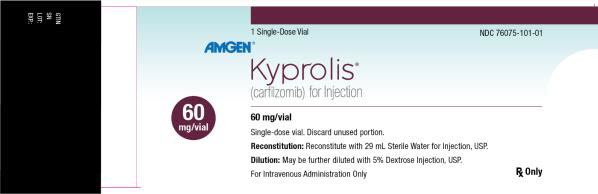 DRUG LABEL: KYPROLIS
NDC: 76075-101 | Form: INJECTION, POWDER, LYOPHILIZED, FOR SOLUTION
Manufacturer: Onyx Pharmaceuticals, Inc.
Category: prescription | Type: HUMAN PRESCRIPTION DRUG LABEL
Date: 20250618

ACTIVE INGREDIENTS: CARFILZOMIB 60 mg/30 mL
INACTIVE INGREDIENTS: BETADEX SULFOBUTYL ETHER SODIUM; ANHYDROUS CITRIC ACID; SODIUM HYDROXIDE; WATER

HIGHLIGHTS OF PRESCRIBING INFORMATION

These highlights do not include all the information needed to use KYPROLIS safely and effectively. See full prescribing information for KYPROLIS.
KYPROLIS® (carfilzomib) for injection, for intravenous use
Initial U.S. Approval: 2012

1 INDICATIONS AND USAGE

Kyprolis is a proteasome inhibitor that is indicated:

- for the treatment of adult patients with relapsed or refractory multiple myeloma who have received one to three lines of therapy in combination with
  - Lenalidomide and dexamethasone; or
  - Dexamethasone; or
  - Daratumumab and dexamethasone; or
  - Daratumumab and hyaluronidase-fihj and dexamethasone; or
  - Isatuximab and dexamethasone. (1, 14)
- as a single agent for the treatment of patients with relapsed or refractory multiple myeloma who have received one or more lines of therapy. (1, 14)

2 DOSAGE AND ADMINISTRATION

- Hydrate prior to and following Kyprolis as needed. (2.1)
- Premedicate prior to all Cycle 1 doses and if infusion-related reactions develop or reappear. (2.1)
- The recommended dosing regimens are as follows. See Full Prescribing Information for additional dosage information. (2.2)

Regimen | Dosage | Infusion Time
Kyprolis and Dexamethasone (Kd) or Kyprolis, Daratumumab and Dexamethasone (DKd) or Kyprolis, Daratumumab and hyaluronidase-fihj and Dexamethasone (DKd) | 20/70 mg/m^2 once weekly | 30 minutes
Kyprolis and Dexamethasone (Kd) or Kyprolis, Daratumumab and Dexamethasone (DKd) or Kyprolis, Daratumumab and hyaluronidase-fihj and Dexamethasone (DKd) or Kyprolis, Isatuximab and Dexamethasone (Isa-Kd) or Kyprolis Monotherapy | 20/56 mg/m^2 twice weekly | 30 minutes
Kyprolis, Lenalidomide and Dexamethasone (KRd) or Kyprolis Monotherapy | 20/27 mg/m^2 twice weekly | 10 minutes

3 DOSAGE FORMS AND STRENGTHS

For injection: 10 mg, 30 mg or 60 mg lyophilized powder in single-dose vial for reconstitution. (3)

4 CONTRAINDICATIONS

None. (4)

5 WARNINGS AND PRECAUTIONS

- Cardiac Toxicities: Monitor for signs and symptoms of cardiac failure or ischemia. Withhold Kyprolis and evaluate promptly. (5.1)
- Acute Renal Failure: Monitor serum creatinine regularly. (5.2)
- Tumor Lysis Syndrome (TLS): Administer pre-treatment hydration. (2.1) Monitor for TLS, including uric acid levels and treat promptly. (5.3)
- Pulmonary Toxicity, including Acute Respiratory Distress Syndrome, Acute Respiratory Failure, and Acute Diffuse Infiltrative Pulmonary Disease: Withhold Kyprolis and evaluate promptly. (5.4)
- Pulmonary Hypertension: Withhold Kyprolis and evaluate. (5.5)
- Dyspnea: For severe or life-threatening dyspnea, withhold Kyprolis and evaluate. (5.6)
- Hypertension, including Hypertensive Crisis: Monitor blood pressure regularly. If hypertension cannot be controlled, interrupt treatment with Kyprolis. (5.7)
- Venous Thrombosis: Thromboprophylaxis is recommended. (5.8)
- Infusion-related Reactions: Premedicate with dexamethasone. (2.1, 5.9)
- Hemorrhage: Fatal or serious cases of hemorrhage may occur, including gastrointestinal, pulmonary, and intracranial hemorrhage. Promptly evaluate signs and symptoms of blood loss. (5.10)
- Thrombocytopenia: Monitor platelet counts; interrupt or reduce Kyprolis dosing as clinically indicated. (2.3, 5.11)
- Hepatic Toxicity and Hepatic Failure: Monitor liver enzymes regularly. Withhold Kyprolis if suspected. (5.12)
- Thrombotic Microangiopathy: Monitor for signs and symptoms. Discontinue Kyprolis if suspected. (5.13)
- Posterior Reversible Encephalopathy Syndrome (PRES): Consider neuro-radiological imaging (MRI) for onset of visual or neurological symptoms; discontinue Kyprolis if suspected. (5.14)
- Progressive Multifocal Leukoencephalopathy: Consider PML if new or worsening neurologic manifestations. Discontinue Kyprolis in patients who develop PML. (5.15)
- Increased Fatal and Serious Toxicities in Combination with Melphalan and Prednisone in Newly Diagnosed Transplant-Ineligible Patients (5.16)
- Embryo-Fetal Toxicity: Kyprolis can cause fetal harm. Advise females of reproductive potential and males with female partners of reproductive potential of potential risk to a fetus and to use effective contraception. (5.17, 8.1)

6 ADVERSE REACTIONS

- The most common adverse reactions occurring in at least 20% of patients treated with Kyprolis in monotherapy trials: anemia, fatigue, thrombocytopenia, nausea, pyrexia, dyspnea, diarrhea, headache, cough, edema peripheral. (6)
- The most common adverse reactions occurring in at least 20% of patients treated with Kyprolis in the combination therapy trials: anemia, diarrhea, hypertension, fatigue, upper respiratory tract infection, thrombocytopenia, pyrexia, cough, dyspnea, and insomnia. (6)

To report SUSPECTED ADVERSE REACTIONS, contact Amgen Medical Information at 1-800-77-AMGEN (1-800-772-6436) or FDA at 1-800-FDA-1088 or www.fda.gov/medwatch.

8 USE IN SPECIFIC POPULATIONS

- Geriatric Use: In the Kyprolis clinical trials, the incidence of adverse reactions was greater in patients ≥ 75 years of age. (8.5)
- Hepatic Impairment: Reduce the dose of Kyprolis by 25% in patients with mild or moderate hepatic impairment. (2.4)
- Patients on Hemodialysis: Administer Kyprolis after the hemodialysis procedure. (2.1)
- Lactation: Advise women not to breastfeed. (8.2)

FULL PRESCRIBING INFORMATION

1 INDICATIONS AND USAGE

1.1 Relapsed or Refractory Multiple Myeloma

- Kyprolis is indicated for the treatment of adult patients with relapsed or refractory multiple myeloma who have received one to three lines of therapy in combination with:
  - Lenalidomide and dexamethasone; or
  - Dexamethasone; or
  - Daratumumab and dexamethasone; or
  - Daratumumab and hyaluronidase-fihj and dexamethasone; or
  - Isatuximab and dexamethasone.
- Kyprolis is indicated as a single agent for the treatment of adult patients with relapsed or refractory multiple myeloma who have received one or more lines of therapy.

2 DOSAGE AND ADMINISTRATION

2.1 Administration Precautions

Hydration

Adequate hydration is required prior to dosing in Cycle 1, especially in patients at high-risk of tumor lysis syndrome (TLS) or renal toxicity. Consider hydration with both oral fluids (30 mL per kg at least 48 hours before Cycle 1, Day 1) and intravenous fluids (250 mL to 500 mL of appropriate intravenous fluid prior to each dose in Cycle 1). If needed, give an additional 250 mL to 500 mL of intravenous fluids following Kyprolis administration. Continue oral and/or intravenous hydration, as needed, in subsequent cycles.

Monitor patients for evidence of volume overload and adjust hydration to individual patient needs, especially in patients with or at risk for cardiac failure [see Warnings and Precautions (5.1, 5.3)].

Electrolyte Monitoring

Monitor serum potassium levels regularly during treatment with Kyprolis [see Adverse Reactions (6.1)].

Premedications and Concomitant Medications

Premedicate with the recommended dose of dexamethasone for monotherapy or dexamethasone administered as part of the combination therapy [see Dosage and Administration (2.2)]. Administer dexamethasone orally or intravenously at least 30 minutes but no more than 4 hours prior to all doses of Kyprolis during Cycle 1 to reduce the incidence and severity of infusion-related reactions [see Warnings and Precautions (5.9)]. Reinstate dexamethasone premedication if these symptoms occur during subsequent cycles.

Provide thromboprophylaxis for patients being treated with Kyprolis in combination with other therapies [see Warnings and Precautions (5.8)].

Consider antiviral prophylaxis to decrease the risk of herpes zoster reactivation [see Adverse Reactions (6.1)].

Dose Calculation

For patients with body surface area (BSA) of 2.2 m^2 or less, calculate the Kyprolis dose using actual BSA. Dose adjustments do not need to be made for weight changes of 20% or less.

For patients with a BSA greater than 2.2 m^2, calculate the Kyprolis dose using a BSA of 2.2 m^2.

2.2 Recommended Dosage

Once Weekly 20/70 mg/m^2 (30-minute infusion)

Kyprolis once weekly 20/70 mg/m^2 administered in combination with

- dexamethasone (Kd),
- daratumumab plus dexamethasone (DKd), or
- daratumumab and hyaluronidase-fihj plus dexamethasone (DKd).

The recommended starting dosage of Kyprolis is 20 mg/m^2 on Cycle 1, Day 1. If tolerated, escalate the dose to 70 mg/m^2 on Cycle 1, Day 8. Administer Kyprolis intravenously as a 30-minute infusion on Days 1, 8, and 15 of each 28-day cycle until disease progression or unacceptable toxicity as shown in Table 1 [see Clinical Studies (14.2)]. Administer dexamethasone 30 minutes to 4 hours before Kyprolis and 1 to 3 hours before daratumumab or daratumumab and hyaluronidase-fihj. For dosage instructions of combination agents with Kyprolis, see Clinical Studies sections 14.2 (Kd) and 14.3 (DKd). Refer to the Prescribing Information for dexamethasone, intravenous daratumumab, and subcutaneous daratumumab and hyaluronidase-fihj for additional dosage information.

Table 1: Kyprolis 20/70 mg/m^2 Once Weekly (30-Minute Infusion)
 | Cycle 1
 | Week 1 |  |  | Week 2 |  |  | Week 3 |  |  | Week 4
 | Day 1 | Day 2 | Days 3-7 | Day 8 | Day 9 | Days 10-14 | Day 15 | Day 16 | Days 17-21 | Day 22 | Day 23 | Days 24-28
Kyprolis (mg/m^2) | 20 | - | - | 70 | - | - | 70 | - | - | - | - | -
 | Cycles 2 and later
 | Week 1 |  |  | Week 2 |  |  | Week 3 |  |  | Week 4
 | Day 1 | Day 2 | Days 3-7 | Day 8 | Day 9 | Days 10-14 | Day 15 | Day 16 | Days 17-21 | Day 22 | Day 23 | Days 24-28
Kyprolis (mg/m^2) | 70 | - | - | 70 | - | - | 70 | - | - | - | - | -

Twice Weekly 20/56 mg/m^2 (30-minute infusion)

Kyprolis twice weekly 20/56 mg/m^2 administered as monotherapy or in combination with

- dexamethasone (Kd),
- daratumumab plus dexamethasone (DKd),
- daratumumab and hyaluronidase-fihj plus dexamethasone (DKd), or
- isatuximab plus dexamethasone (Isa-Kd).

The recommended starting dosage of Kyprolis is 20 mg/m^2 on Cycle 1, Days 1 and 2. If tolerated, escalate the dose to 56 mg/m^2 on Cycle 1, Day 8. Administer Kyprolis intravenously as a 30-minute infusion on Days 1, 2, 8, 9, 15, and 16 of each 28-day cycle as shown in Table 2 until disease progression or unacceptable toxicity [see Clinical Studies (Section 14)]. If given as monotherapy, administer 8 mg dexamethasone orally or intravenously 30 minutes to 4 hours before Kyprolis then as needed to minimize infusion-related reactions [see Dosage and Administration (2.1)]. Kyprolis given as monotherapy may be omitted on Days 8 and 9 of cycle 13 onward. For dosage instructions of combination agents administered with Kyprolis, see Clinical Studies sections 14.2 (Kd), 14.3 (DKd), 14.4 (Isa-Kd), and 14.5 (Monotherapy). Refer to the Prescribing Information for dexamethasone, intravenous daratumumab, subcutaneous daratumumab and hyaluronidase-fihj, and isatuximab for additional dosage information.

Table 2: Kyprolis 20/56 mg/m^2 Twice Weekly (30-Minute Infusion)
 | Cycle 1
 | Week 1 |  |  | Week 2 |  |  | Week 3 |  |  | Week 4
 | Day 1 | Day 2 | Days 3-7 | Day 8 | Day 9 | Days 10-14 | Day 15 | Day 16 | Days 17-21 | Day 22 | Day 23 | Days 24-28
Kyprolis [As monotherapy, dexamethasone premedication is required for each Kyprolis dose in Cycle 1.] (mg/m^2) | 20 | 20 | - | 56 | 56 | - | 56 | 56 | - | - | - | -
 | Cycles 2 and later
 | Week 1 |  |  | Week 2 |  |  | Week 3 |  |  | Week 4
 | Day 1 | Day 2 | Days 3-7 | Day 8 | Day 9 | Days 10-14 | Day 15 | Day 16 | Days 17-21 | Day 22 | Day 23 | Days 24-28
Kyprolis (mg/m^2) | 56 | 56 | - | 56 | 56 | - | 56 | 56 | - | - | - | -

Twice Weekly 20/27 mg/m^2 (10-minute infusion)

Kyprolis twice weekly 20/27 mg/m^2 is administered as monotherapy or in combination with lenalidomide and dexamethasone (KRd).

The recommended starting dosage of Kyprolis is 20 mg/m^2 in Cycle 1 on Days 1 and 2. If tolerated, escalate the dose to 27 mg/m^2 on Day 8 of Cycle 1 and thereafter. Administer Kyprolis intravenously as a 10-minute infusion [see Clinical Studies (14.4)]. In Cycles 1 through 12, administer Kyprolis on Days 1, 2, 8, 9, 15 and 16 of each 28-day cycle as shown in Table 3. From Cycle 13, administer Kyprolis on Days 1, 2, 15 and 16 of each 28-day cycle. If given as monotherapy, premedicate with dexamethasone 4 mg orally or intravenously 30 minutes to 4 hours before each Kyprolis dose in Cycle 1, then as needed to minimize infusion-related reactions [see Dosage and Administration (2.1)]. Continue Kyprolis with the regimens shown in Table 3 until disease progression or unacceptable toxicity occurs. When combined with lenalidomide and dexamethasone, discontinue Kyprolis after Cycle 18 and continue lenalidomide and dexamethasone until disease progression or unacceptable toxicity occurs. For dosage instructions of combination agents with Kyprolis, see Clinical Studies sections 14.1 (KRd) and 14.5 (Monotherapy). Refer to the Prescribing Information for dexamethasone and lenalidomide for additional dosage information.

Table 3: Kyprolis 20/27 mg/m^2 Twice Weekly (10-Minute Infusion)
 | Cycle 1
 | Week 1 |  |  | Week 2 |  |  | Week 3 |  |  | Week 4
 | Day 1 | Day 2 | Days 3-7 | Day 8 | Day 9 | Days 10-14 | Day 15 | Day 16 | Days 17-21 | Days 22-28
Kyprolis (mg/m^2) [Dexamethasone premedication is required for each Kyprolis dose in Cycle 1.] | 20 | 20 | - | 27 | 27 | - | 27 | 27 | - | -
 | Cycles 2 to 12
 | Week 1 |  |  | Week 2 |  |  | Week 3 |  |  | Week 4
 | Day 1 | Day 2 | Days 3-7 | Day 8 | Day 9 | Days 10-14 | Day 15 | Day 16 | Days 17-21 | Days 22-28
Kyprolis (mg/m^2) | 27 | 27 | - | 27 | 27 | - | 27 | 27 | - | -
 | Cycles 13 and later [When administered in combination with lenalidomide and dexamethasone, discontinue Kyprolis after Cycle 18.]
 | Week 1 |  |  | Week 2 |  |  | Week 3 |  |  | Week 4
 | Day 1 | Day 2 | Days 3-7 | Day 8 | Day 9 | Days 10-14 | Day 15 | Day 16 | Days 17-21 | Days 22-28
Kyprolis (mg/m^2) | 27 | 27 | - | - | - | - | 27 | 27 | - | -

2.3 Dosage Modifications for Adverse Reactions

Recommended actions and dosage modifications for Kyprolis are presented in Table 4. Dose level reductions are presented in Table 5. See the lenalidomide, intravenous daratumumab, subcutaneous daratumumab and hyaluronidase-fihj, isatuximab, and dexamethasone Prescribing Information respectively for recommended dosage modifications associated with each product.

Table 4: Dosage Modifications for Adverse Reactions [See Table 10 for dose level reductions.]
Hematologic Toxicity [see Warnings and Precautions (5.11), Adverse Reactions (6.1)] | Recommended Action
- ANC less than 0.5 × 10^9/L | - Withhold dose - If recovered to greater than or equal to 0.5 × 10^9/L, continue at the same dose level - For subsequent drops to less than 0.5 × 10^9/L, follow the same recommendations as above and consider 1 dose level reduction when restarting Kyprolis
- Febrile neutropenia: ANC less than 0.5 × 10^9/L and an oral temperature more than 38.5°C or two consecutive readings of more than 38.0°C for 2 hours | - Withhold dose - If ANC returns to baseline grade and fever resolves, resume at the same dose level
- Platelets less than 10 × 10^9/L or evidence of bleeding with thrombocytopenia | - Withhold dose - If recovered to greater than or equal to 10 × 10^9/L and/or bleeding is controlled, continue at the same dose level - For subsequent drops to less than 10 × 10^9/L, follow the same recommendations as above and consider 1 dose level reduction when restarting Kyprolis
Renal Toxicity [see Warnings and Precautions (5.2)] | Recommended Action
- Serum creatinine greater than or equal to 2 × baseline, or - Creatinine clearance less than 15 mL/min, or creatinine clearance decreases to less than or equal to 50% of baseline, or need for hemodialysis | - Withhold dose and continue monitoring renal function (serum creatinine or creatinine clearance) - If attributable to Kyprolis, resume when renal function has recovered to within 25% of baseline; start at 1 dose level reduction - If not attributable to Kyprolis, dosing may be resumed at the discretion of the healthcare provider - For patients on hemodialysis receiving Kyprolis, the dose is to be administered after the hemodialysis procedure
Other Non-hematologic Toxicity [see Adverse Reactions (6.1)]. | Recommended Action
- All other severe or life-threatening [Grade 3 and 4.] non-hematological toxicities | - Withhold until resolved or returned to baseline - Consider restarting the next scheduled treatment at 1 dose level reduction
ANC = absolute neutrophil count

Table 5: Dose Level Reductions for Adverse Reactions
Regimen | Kyprolis Frequency | Dose | First Dose Reduction | Second Dose Reduction | Third Dose Reduction
Kyprolis and Dexamethasone OR Kyprolis, Daratumumab, and Dexamethasone | Once weekly | 70 mg/m^2 | 56 mg/m^2 | 45 mg/m^2 | 36 mg/m^2 [If toxicity persists, discontinue Kyprolis treatment.]
Kyprolis and Dexamethasone OR Kyprolis, Daratumumab, and Dexamethasone OR Kyprolis, Isatuximab, and Dexamethasone OR Kyprolis Monotherapy | Twice weekly | 56 mg/m^2 | 45 mg/m^2 | 36 mg/m^2 | 27 mg/m^2
Kyprolis, Lenalidomide, and Dexamethasone OR Kyprolis Monotherapy | Twice weekly | 27 mg/m^2 | 20 mg/m^2 | 15 mg/m^2 | —
Note: Infusion times remain unchanged during dose reduction(s).

2.4 Dosage Modifications for Hepatic Impairment

For patients with mild (total bilirubin 1 to 1.5 × ULN and any AST or total bilirubin ≤ ULN and AST > ULN) or moderate (total bilirubin > 1.5 to 3 × ULN and any AST) hepatic impairment, reduce the dose of Kyprolis by 25% [see Use in Specific Populations (8.6), Clinical Pharmacology (12.3)].

2.5 Recommended Dosage for End Stage Renal Disease

For patients with end stage renal disease who are on hemodialysis, administer Kyprolis after the hemodialysis procedure.

2.6 Preparation and Administration

Kyprolis vials contain no antimicrobial preservatives and are intended for single-dose only. The reconstituted solution contains carfilzomib at a concentration of 2 mg/mL.

Read the complete preparation instructions prior to reconstitution. Parenteral drug products should be inspected visually for particulate matter and discoloration prior to administration, whenever solution and container permit.

Reconstitution/Preparation Steps:

1. Remove vial from refrigerator just prior to use.
2. Calculate the dose (mg/m^2) and number of vials of Kyprolis required using the patient's BSA at baseline.
3. Aseptically reconstitute each Kyprolis vial only with Sterile Water for Injection, USP using the volumes described in Table 6. Use a 21-gauge or larger needle (0.8 mm or smaller external diameter needle) to reconstitute each vial by slowly injecting Sterile Water for Injection through the stopper and directing the Sterile Water for Injection onto the INSIDE WALL OF THE VIAL to minimize foaming. There is no data to support the use of closed system transfer devices with Kyprolis.
  Table 6: Reconstitution Volumes
  Strength | Amount of Sterile Water for Injection required for reconstitution
  10 mg vial | 5 mL
  30 mg vial | 15 mL
  60 mg vial | 29 mL
4. Gently swirl and/or invert the vial slowly for about 1 minute, or until complete dissolution. DO NOT SHAKE to avoid foam generation. If foaming occurs, allow the solution to settle in the vial until foaming subsides (approximately 5 minutes) and the solution is clear.
5. Visually inspect for particulate matter and discoloration prior to administration. The reconstituted product should be a clear, colorless solution and should not be administered if any discoloration or particulate matter is observed.
6. Discard any unused portion left in the vial. DO NOT pool unused portions from the vials. DO NOT administer more than one dose from a vial.
7. Administer Kyprolis directly by intravenous infusion or in a 50 mL to 100 mL intravenous bag containing 5% Dextrose Injection. Do not administer as an intravenous push or bolus.
8. When administering in an intravenous bag, use a 21-gauge or larger gauge needle (0.8 mm or smaller external diameter needle) to withdraw the calculated dose from the vial and dilute into 50 mL or 100 mL intravenous bag containing only 5% Dextrose Injection (based on the calculated total dose and infusion time).
9. Flush the intravenous administration line with 0.9% Sodium Chloride Injection or 5% Dextrose Injection immediately before and after Kyprolis administration.
10. Do not mix Kyprolis with or administer as an infusion with other medicinal products.

The stabilities of reconstituted Kyprolis under various temperature and container conditions are shown in Table 7.

Table 7: Stability of Reconstituted Kyprolis
Storage Conditions of Reconstituted Kyprolis | Stability [Total time from reconstitution to administration should not exceed 24 hours.] per Container
Storage Conditions of Reconstituted Kyprolis | Vial | Syringe | Intravenous Bag (D5W [5% Dextrose Injection.])
Refrigerated 2°C to 8°C (36°F to 46°F) | 24 hours | 24 hours | 24 hours
Room Temperature 15°C to 30°C (59°F to 86°F) | 4 hours | 4 hours | 4 hours

3 DOSAGE FORMS AND STRENGTHS

For injection: 10 mg, 30 mg and 60 mg as a white to off-white lyophilized cake or powder in single-dose vial for reconstitution.

4 CONTRAINDICATIONS

None.

5 WARNINGS AND PRECAUTIONS

5.1 Cardiac Toxicities

New onset or worsening of pre-existing cardiac failure (e.g., congestive heart failure, pulmonary edema, decreased ejection fraction), cardiomyopathy, myocardial ischemia, and myocardial infarction including fatalities have occurred following administration of Kyprolis. Some events occurred in patients with normal baseline ventricular function. In clinical studies with Kyprolis, these events occurred throughout the course of Kyprolis therapy. Death due to cardiac arrest has occurred within one day of Kyprolis administration. In randomized, open-label, multicenter trials for combination therapies, the incidence of cardiac failure events was 8% and that of arrythmias was 8% (majority of which were atrial fibrillation and sinus tachycardia) [see Adverse Reactions (6.1)].

Monitor patients for clinical signs or symptoms of cardiac failure or cardiac ischemia. Evaluate promptly if cardiac toxicity is suspected. Withhold Kyprolis for Grade 3 or 4 cardiac adverse reactions until recovery and consider whether to restart Kyprolis at 1 dose level reduction based on a benefit/risk assessment [see Dosage and Administration (2.3)].

While adequate hydration is required prior to each dose in Cycle 1, monitor all patients for evidence of volume overload, especially patients at risk for cardiac failure. Adjust total fluid intake as clinically appropriate in patients with baseline cardiac failure or who are at risk for cardiac failure [see Dosage and Administration (2.1)].

In patients ≥ 75 years of age, the risk of cardiac failure is increased compared to younger patients. Patients with New York Heart Association Class III and IV heart failure, recent myocardial infarction, conduction abnormalities, angina, or arrhythmias uncontrolled by medications were not eligible for the clinical trials. These patients may be at greater risk for cardiac complications; for these patients, complete a comprehensive medical assessment (including blood pressure control and fluid management) prior to starting treatment with Kyprolis and remain under close follow-up [see Use in Specific Populations (8.5)].

5.2 Acute Renal Failure

Cases of acute renal failure have occurred in patients receiving Kyprolis. Some of these events have been fatal. Renal insufficiency (including renal failure) has occurred in approximately 9% of patients who received Kyprolis. Acute renal failure was reported more frequently in patients with advanced relapsed and refractory multiple myeloma who received Kyprolis monotherapy. The risk of fatal renal failure was greater in patients with a baseline reduced estimated creatinine clearance (calculated using Cockcroft-Gault equation).

Monitor renal function with regular measurement of the serum creatinine and/or estimated creatinine clearance. Reduce or withhold dose as appropriate [see Dosage and Administration (2.3)].

5.3 Tumor Lysis Syndrome

Cases of TLS, including fatal outcomes, have been reported in patients who received Kyprolis. Patients with multiple myeloma and a high tumor burden should be considered to be at greater risk for TLS.

Administer oral and intravenous fluids before administration of Kyprolis in Cycle 1 and in subsequent cycles as needed. Consider uric acid-lowering drugs in patients at risk for TLS. Monitor for TLS during treatment and manage promptly, including interruption of Kyprolis until TLS is resolved [see Dosage and Administration (2.1)].

5.4 Pulmonary Toxicity

Acute Respiratory Distress Syndrome (ARDS) and acute respiratory failure have occurred in approximately 2% of patients who received Kyprolis. In addition, acute diffuse infiltrative pulmonary disease, such as pneumonitis and interstitial lung disease, occurred in approximately 2% of patients who received Kyprolis. Some events were fatal.

In the event of drug-induced pulmonary toxicity, discontinue Kyprolis.

5.5 Pulmonary Hypertension

Pulmonary arterial hypertension was reported in approximately 2% of patients who received Kyprolis, with Grade 3 or greater in less than 1%.

Evaluate with cardiac imaging and/or other tests as indicated. Withhold Kyprolis for pulmonary hypertension until resolved or returned to baseline and consider whether to restart Kyprolis based on a benefit/risk assessment.

5.6 Dyspnea

Dyspnea was reported in 25% of patients treated with Kyprolis, with Grade 3 or greater in 4%.

Evaluate dyspnea to exclude cardiopulmonary conditions including cardiac failure and pulmonary syndromes. Stop Kyprolis for Grade 3 or 4 dyspnea until resolved or returned to baseline. Consider whether to restart Kyprolis based on a benefit/risk assessment [see Warnings and Precautions (5.1, 5.4) and Adverse Reactions (6.1)].

5.7 Hypertension

Hypertension, including hypertensive crisis and hypertensive emergency, has been observed with Kyprolis. In ASPIRE, the incidence of hypertension events was 17% in the KRd arm versus 9% in the Rd arm. In ENDEAVOR, the incidence of hypertension events was 34% in the Kd arm versus 11% in the Vd arm. In CANDOR, the incidence of hypertension events was 31% in the DKd arm versus 28% in the Kd arm. Some of these events have been fatal.

Optimize blood pressure prior to starting Kyprolis. Monitor blood pressure regularly in all patients while on Kyprolis. If hypertension cannot be adequately controlled, withhold Kyprolis and evaluate. Consider whether to restart Kyprolis based on a benefit/risk assessment.

5.8 Venous Thrombosis

Venous thromboembolic events (including deep venous thrombosis and pulmonary embolism) have been observed with Kyprolis. In ASPIRE, with thromboprophylaxis used in both arms, the incidence of venous thromboembolic events in the first 12 cycles was 13% in the KRd arm versus 6% in the Rd arm. In ENDEAVOR, the incidence of venous thromboembolic events in months 1–6 was 9% in the Kd arm versus 2% in the Vd arm. With Kyprolis monotherapy, the incidence of venous thromboembolic events was 2% [see Adverse Reactions (6.1)].

Provide thromboprophylaxis for patients being treated with Kyprolis in combination with lenalidomide and dexamethasone; with dexamethasone; or with intravenous daratumumab and dexamethasone. Select the thromboprophylaxis regimen based on the patient's underlying risks.

For patients using oral contraceptives or hormonal contraception associated with a risk of thrombosis, consider non-hormonal contraception during treatment when Kyprolis is administered in combination [see Use in Specific Populations (8.3)].

5.9 Infusion-Related Reactions

Infusion-related reactions, including life-threatening reactions, have occurred in patients receiving Kyprolis. Signs and symptoms include fever, chills, arthralgia, myalgia, facial flushing, facial edema, laryngeal edema, vomiting, weakness, shortness of breath, hypotension, syncope, chest tightness, or angina. These reactions can occur immediately following or up to 24 hours after administration of Kyprolis.

Administer dexamethasone prior to Kyprolis to reduce the incidence and severity of infusion-related reactions [see Dosage and Administration (2.1, 2.2), Adverse Reactions (6.1)].

5.10 Hemorrhage

Fatal or serious cases of hemorrhage have been reported in patients treated with Kyprolis [see Adverse Reactions (6.1)]. Hemorrhagic events have included gastrointestinal, pulmonary, and intracranial hemorrhage and epistaxis. The bleeding can be spontaneous and intracranial hemorrhage has occurred without trauma. Hemorrhage has been reported in patients having either low or normal platelet counts. Hemorrhage has also been reported in patients who were not on antiplatelet therapy or anticoagulation.

Promptly evaluate signs and symptoms of blood loss. Reduce or withhold dose as appropriate [see Dosage and Administration (2.3)].

5.11 Thrombocytopenia

Kyprolis causes thrombocytopenia with platelet nadirs observed between Day 8 and Day 15 of each 28-day cycle, with recovery to baseline platelet count usually by the start of the next cycle [see Adverse Reactions (6.1)]. Thrombocytopenia was reported in approximately 32% of patients in clinical trials with Kyprolis. Hemorrhage may occur [see Adverse Reactions (6.1), Warnings and Precautions (5.10)].

Monitor platelet counts frequently during treatment with Kyprolis. Reduce or withhold dose as appropriate [see Dosage and Administration (2.3)].

5.12 Hepatic Toxicity and Hepatic Failure

Cases of hepatic failure, including fatal cases, have been reported (2%) during treatment with Kyprolis. Kyprolis can cause increased serum transaminases [see Adverse Reactions (6.1)].

Monitor liver enzymes regularly, regardless of baseline values. Reduce or withhold dose as appropriate [see Dosage and Administration (2.3)].

5.13 Thrombotic Microangiopathy

Cases of thrombotic microangiopathy, including thrombotic thrombocytopenic purpura/ hemolytic uremic syndrome (TTP/HUS), have been reported in patients who received Kyprolis. Some of these events have been fatal.

Monitor for signs and symptoms of TTP/HUS. If the diagnosis is suspected, stop Kyprolis and evaluate. If the diagnosis of TTP/HUS is excluded, Kyprolis may be restarted. The safety of reinitiating Kyprolis therapy in patients previously experiencing TTP/HUS is not known.

5.14 Posterior Reversible Encephalopathy Syndrome

Cases of posterior reversible encephalopathy syndrome (PRES) have been reported in patients receiving Kyprolis. PRES, formerly termed Reversible Posterior Leukoencephalopathy Syndrome (RPLS), is a neurological disorder which can present with seizure, headache, lethargy, confusion, blindness, altered consciousness, and other visual and neurological disturbances, along with hypertension, and the diagnosis is confirmed by neuro-radiological imaging (MRI).

Discontinue Kyprolis if PRES is suspected and evaluate. The safety of reinitiating Kyprolis therapy in patients previously experiencing PRES is not known.

5.15 Progressive Multifocal Leukoencephalopathy

Progressive multifocal leukoencephalopathy (PML), which can be fatal, has been reported with Kyprolis. In addition to Kyprolis, other possible contributory factors include prior or concurrent immunosuppressive therapy that may cause immunosuppression.

Consider PML in any patient with new onset of or changes in pre-existing neurological signs or symptoms. If PML is suspected, discontinue Kyprolis and initiate evaluation for PML including neurology consultation.

5.16 Increased Fatal and Serious Toxicities in Combination with Melphalan and Prednisone in Newly Diagnosed Transplant-Ineligible Patients

In CLARION, a clinical trial of 955 transplant-ineligible patients with newly diagnosed multiple myeloma randomized to Kyprolis (20/36 mg/m^2 by 30-minute infusion twice weekly for four of each six-week cycle), melphalan and prednisone (KMP) or bortezomib, melphalan and prednisone (VMP), a higher incidence of fatal adverse reactions (7% versus 4%) and serious adverse reactions (50% versus 42%) were observed in the KMP arm compared to patients in the VMP arm, respectively. Patients in the KMP arm were observed to have a higher incidence of any grade adverse reactions involving cardiac failure (11% versus 4%), hypertension (25% versus 8%), acute renal failure (14% versus 6%), and dyspnea (18% versus 9%). This study did not meet its primary outcome measure of superiority in progression-free survival (PFS) for the KMP arm. Kyprolis in combination with melphalan and prednisone is not indicated for transplant-ineligible patients with newly diagnosed multiple myeloma.

5.17 Embryo-Fetal Toxicity

Based on the mechanism of action and findings in animals, Kyprolis can cause fetal harm when administered to a pregnant woman. Carfilzomib administered intravenously to pregnant rabbits during organogenesis at a dose approximately 40% of the clinical dose of 27 mg/m^2 based on BSA caused post-implantation loss and a decrease in fetal weight.

Advise pregnant women of the potential risk to a fetus. Advise females of reproductive potential to use effective contraception during treatment with Kyprolis and for 6 months following the last dose. Advise males with female partners of reproductive potential to use effective contraception during treatment with Kyprolis and for 3 months following the last dose [see Use in Specific Populations (8.1, 8.3), Nonclinical Toxicology (13.1)].

6 ADVERSE REACTIONS

The following clinically significant adverse reactions are described elsewhere in the labeling:

- Cardiac Toxicities [see Warnings and Precautions (5.1)]
- Acute Renal Failure [see Warnings and Precautions (5.2)]
- Tumor Lysis Syndrome [see Warnings and Precautions (5.3)]
- Pulmonary Toxicity [see Warnings and Precautions (5.4)]
- Pulmonary Hypertension [see Warnings and Precautions (5.5)]
- Dyspnea [see Warnings and Precautions (5.6)]
- Hypertension [see Warnings and Precautions (5.7)]
- Venous Thrombosis [see Warnings and Precautions (5.8)]
- Infusion-Related Reactions [see Warnings and Precautions (5.9)]
- Hemorrhage [see Warnings and Precautions (5.10)]
- Thrombocytopenia [see Warnings and Precautions (5.11)]
- Hepatic Toxicity and Hepatic Failure [see Warnings and Precautions (5.12)]
- Thrombotic Microangiopathy [see Warnings and Precautions (5.13)]
- Posterior Reversible Encephalopathy Syndrome [see Warnings and Precautions (5.14)]
- Progressive Multifocal Leukoencephalopathy [see Warnings and Precautions (5.15)]

6.1 Clinical Trials Experience

Because clinical trials are conducted under widely varying conditions, adverse reaction rates observed in the clinical trials of a drug cannot be directly compared with rates in the clinical trials of another drug and may not reflect the rates observed in practice.

The pooled safety population described in the Warnings and Precautions reflect exposure to Kyprolis in 2,239 patients administered in combination with other drugs in ASPIRE, ENDEAVOR, A.R.R.O.W., CANDOR, IKEMA, EQUULEUS, and PLEIADES. The most common adverse reactions occurring in at least 20% of patients who received Kyprolis in combination were anemia, diarrhea, hypertension, fatigue, upper respiratory tract infection, thrombocytopenia, pyrexia, cough, dyspnea, and insomnia.

Kyprolis in Combination with Lenalidomide and Dexamethasone

The safety of Kyprolis 20/27 mg/m^2 twice weekly in combination with lenalidomide and dexamethasone (KRd) was evaluated in ASPIRE [see Clinical Studies (14.1)]. The median number of cycles initiated was 22 cycles for the KRd arm and 14 cycles for the Rd arm.

Deaths due to adverse reactions within 30 days of the last dose of any therapy in the KRd arm occurred in 45/392 (12%) patients compared with 42/389 (11%) patients who died due to adverse reactions within 30 days of the last dose of any Rd therapy. The most frequent cause of deaths occurring in patients (%) in the two arms (KRd versus Rd) included infection 12 (3%) versus 11 (3%), cardiac 10 (3%) versus 9 (2%), and other adverse reactions 23 (6%) versus 22 (6%).

Serious adverse reactions were reported in 65% of the patients in the KRd arm and 57% of the patients in the Rd arm. The most frequent serious adverse reactions reported in the KRd arm as compared with the Rd arm were pneumonia (17% versus 13%), respiratory tract infection (4% versus 2%), pyrexia (4% versus 3%), and pulmonary embolism (3% versus 2%).

Discontinuation due to any adverse reaction occurred in 33% in the KRd arm versus 30% in the Rd arm. Adverse reactions leading to discontinuation of Kyprolis occurred in 12% of patients and the most common reactions included pneumonia (1%), myocardial infarction (0.8%), and upper respiratory tract infection (0.8%). The incidence of cardiac failure events was 7% in the KRd arm versus 4% in the Rd arm.

Table 8 summarizes the adverse reactions in the first 12 cycles in ASPIRE.

Table 8: Adverse Reactions (≥ 10%) Occurring in Cycles 1–12 in Patients Who Received KRd (20/27 mg/m^2 Regimen) in ASPIRE
Adverse Reactions | KRd (N = 392) n (%) |  | Rd (N = 389) n (%)
Adverse Reactions | Any Grade | ≥ Grade 3 | Any Grade | ≥ Grade 3
Blood and Lymphatic System Disorders
Anemia | 138 (35) | 53 (14) | 127 (33) | 47 (12)
Neutropenia | 124 (32) | 104 (27) | 115 (30) | 89 (23)
Thrombocytopenia | 100 (26) | 58 (15) | 75 (19) | 39 (10)
Gastrointestinal Disorders
Diarrhea | 119 (30) | 8 (2) | 106 (27) | 12 (3)
Constipation | 68 (17) | 0 (0) | 55 (14) | 1 (0)
Nausea | 63 (16) | 1 (0) | 43 (11) | 3 (1)
General Disorders and Administration Site Conditions
Fatigue | 113 (29) | 23 (6) | 107 (28) | 20 (5)
Pyrexia | 93 (24) | 5 (1) | 64 (17) | 1 (0)
Edema peripheral | 59 (15) | 3 (1) | 48 (12) | 2 (1)
Asthenia | 54 (14) | 11 (3) | 49 (13) | 7 (2)
Infections
Upper respiratory tract infection | 87 (22) | 7 (2) | 54 (14) | 4 (1)
Bronchitis | 55 (14) | 5 (1) | 40 (10) | 2 (1)
Viral upper respiratory tract infection | 55 (14) | 0 (0) | 44 (11) | 0 (0)
Pneumonia [Pneumonia includes pneumonia and bronchopneumonia.] | 54 (14) | 35 (9) | 43 (11) | 27 (7)
Metabolism and Nutrition Disorders
Hypokalemia | 78 (20) | 22 (6) | 35 (9) | 12 (3)
Hypocalcemia | 55 (14) | 10 (3) | 39 (10) | 5 (1)
Hyperglycemia | 43 (11) | 18 (5) | 33 (9) | 15 (4)
Musculoskeletal and Connective Tissue Disorders
Muscle spasms | 92 (24) | 3 (1) | 75 (19) | 3 (1)
Back pain | 41 (11) | 4 (1) | 54 (14) | 6 (2)
Nervous System Disorders
Peripheral neuropathies [Peripheral neuropathies includes peripheral neuropathy, peripheral sensory neuropathy, and peripheral motor neuropathy.] | 43 (11) | 7 (2) | 39 (10) | 4 (1)
Psychiatric Disorders
Insomnia | 64 (16) | 6 (2) | 51 (13) | 8 (2)
Respiratory, Thoracic and Mediastinal Disorders
Cough [Cough includes cough and productive cough.] | 93 (24) | 2 (1) | 54 (14) | 0 (0)
Dyspnea [Dyspnea includes dyspnea and dyspnea exertional.] | 71 (18) | 8 (2) | 61 (16) | 6 (2)
Skin and Subcutaneous Tissue Disorders
Rash | 45 (12) | 5 (1) | 54 (14) | 5 (1)
Vascular Disorders
Embolic and thrombotic events [Embolic and thrombotic events, venous includes deep vein thrombosis, pulmonary embolism, thrombophlebitis superficial, thrombophlebitis, venous thrombosis limb, post thrombotic syndrome, venous thrombosis.] | 49 (13) | 16 (4) | 23 (6) | 9 (2)
Hypertension [Hypertension includes hypertension, hypertensive crisis.] | 41 (11) | 12 (3) | 15 (4) | 4 (1)
KRd = Kyprolis, lenalidomide, and dexamethasone; Rd = lenalidomide and dexamethasone

There were 274 (70%) patients in the KRd arm who received treatment beyond Cycle 12. There were no new clinically relevant adverse reactions that emerged in the later treatment cycles.

Adverse Reactions Occurring at a Frequency of < 10%

- Blood and lymphatic system disorders: febrile neutropenia, lymphopenia
- Cardiac disorders: cardiac arrest, cardiac failure, cardiac failure congestive, myocardial infarction, myocardial ischemia, pericardial effusion
- Ear and labyrinth disorders: deafness, tinnitus
- Eye disorders: cataract, vision blurred
- Gastrointestinal disorders: abdominal pain, abdominal pain upper, dyspepsia, gastrointestinal hemorrhage, toothache
- General disorders and administration site conditions: chills, infusion site reaction, multi-organ failure, pain
- Infections: clostridium difficile colitis, influenza, lung infection, rhinitis, sepsis, urinary tract infection, viral infection
- Metabolism and nutrition disorders: dehydration, hyperkalemia, hyperuricemia, hypoalbuminemia, hyponatremia, tumor lysis syndrome
- Musculoskeletal and connective tissue disorders: muscular weakness, myalgia
- Nervous system disorders: hypoesthesia, intracranial hemorrhage, paresthesia
- Psychiatric disorders: anxiety, delirium
- Renal and urinary disorders: renal failure, renal failure acute, renal impairment
- Respiratory, thoracic and mediastinal disorders: dysphonia, epistaxis, oropharyngeal pain, pulmonary embolism, pulmonary edema, pulmonary hemorrhage
- Skin and subcutaneous tissue disorders: erythema, hyperhidrosis, pruritus
- Vascular disorders: deep vein thrombosis, hemorrhage, hypotension

Grade 3 and higher adverse reactions that occurred during Cycles 1–12 with a substantial difference (≥ 2%) between the two arms were neutropenia, thrombocytopenia, hypokalemia, and hypophosphatemia.

Table 9 describes Grade 3–4 laboratory abnormalities reported in ASPIRE.

Table 9: Grade 3–4 Laboratory Abnormalities (≥ 10%) in Cycles 1-12 in Patients Who Received KRd (20/27 mg/m^2 Regimen) in ASPIRE
Laboratory Abnormality | KRd (N = 392) n (%) | Rd (N = 389) n (%)
Decreased lymphocytes | 182 (46) | 119 (31)
Decreased absolute neutrophil count | 152 (39) | 141 (36)
Decreased phosphorus | 122 (31) | 106 (27)
Decreased platelets | 101 (26) | 59 (15)
Decreased total white blood cell count | 97 (25) | 71 (18)
Decreased hemoglobin | 58 (15) | 68 (18)
Increased glucose | 53 (14) | 30 (8)
Decreased potassium | 41 (11) | 23 (6)
KRd = Kyprolis, lenalidomide, and dexamethasone; Rd = lenalidomide and dexamethasone

Kyprolis in Combination with Dexamethasone

The safety of Kyprolis in combination with dexamethasone was evaluated in two open-label, randomized trials (ENDEAVOR and A.R.R.O.W.).

ENDEAVOR

The safety of Kyprolis 20/56 mg/m^2 twice weekly in combination with dexamethasone (Kd) was evaluated in ENDEAVOR [see Clinical Studies (14.2)]. Patients received treatment for a median duration of 48 weeks in the Kd arm and 27 weeks in the bortezomib/dexamethasone (Vd) arm.

Deaths due to adverse reactions within 30 days of last study treatment occurred in 32/463 (7%) patients in the Kd arm and 21/456 (5%) patients in the Vd arm. The causes of death occurring in patients (%) in the two arms (Kd versus Vd) included cardiac 4 (1%) versus 5 (1%), infections 8 (2%) versus 8 (2%), disease progression 7 (2%) versus 4 (1%), pulmonary 3 (1%) versus 2 (< 1%), renal 1 (< 1%) versus 0 (0%), and other adverse reactions 9 (2%) versus 2 (< 1%).

Serious adverse reactions were reported in 59% of the patients in the Kd arm and 40% of the patients in the Vd arm. In both arms, pneumonia was the most frequently reported serious adverse reaction (8% versus 9%).

Discontinuation due to any adverse reaction occurred in 29% in the Kd arm versus 26% in the Vd arm. The most frequent adverse reaction leading to discontinuation was cardiac failure in the Kd arm (n = 8, 2%) and peripheral neuropathy in the Vd arm (n = 22, 5%). The incidence of cardiac failure events was 11% in the Kd arm versus 3% in the Vd arm.

Adverse reactions in the first 6 months of therapy that occurred at a rate of 10% or greater in the Kd arm are presented in Table 10.

Table 10: Adverse Reactions (≥ 10%) Occurring in Months 1–6 in Patients Who Received Kd (20/56 mg/m^2 Regimen) in ENDEAVOR
Adverse Reactions | Kd (N = 463) n (%) |  | Vd (N = 456) n (%)
Adverse Reactions | Any Grade | Grade ≥ 3 | Any Grade | Grade ≥ 3
Blood and Lymphatic System Disorders
Anemia | 161 (35) | 57 (12) | 112 (25) | 43 (9)
Thrombocytopenia [Thrombocytopenia includes platelet count decreased and thrombocytopenia.] | 125 (27) | 45 (10) | 112 (25) | 64 (14)
Gastrointestinal Disorders
Diarrhea | 117 (25) | 14 (3) | 149 (33) | 27 (6)
Nausea | 70 (15) | 4 (1) | 68 (15) | 3 (1)
Constipation | 60 (13) | 1 (0) | 113 (25) | 6 (1)
Vomiting | 45 (10) | 5 (1) | 33 (7) | 3 (1)
General Disorders and Administration Site Conditions
Fatigue | 116 (25) | 14 (3) | 126 (28) | 25 (6)
Pyrexia | 102 (22) | 9 (2) | 52 (11) | 3 (1)
Asthenia | 73 (16) | 9 (2) | 65 (14) | 13 (3)
Peripheral edema | 62 (13) | 3 (1) | 62 (14) | 3 (1)
Infections
Upper respiratory tract infection | 67 (15) | 4 (1) | 55 (12) | 3 (1)
Bronchitis | 54 (12) | 5 (1) | 25 (6) | 2 (0)
Musculoskeletal and Connective Tissue Disorders
Muscle spasms | 70 (15) | 1 (0) | 23 (5) | 3 (1)
Back pain | 64 (14) | 8 (2) | 61 (13) | 10 (2)
Nervous System Disorders
Headache | 67 (15) | 4 (1) | 39 (9) | 2 (0)
Peripheral neuropathies [Peripheral neuropathies includes peripheral neuropathy, peripheral sensory neuropathy, and peripheral motor neuropathy.] , [See Clinical Studies (14.2).] | 56 (12) | 7 (2) | 170 (37) | 23 (5)
Psychiatric Disorders
Insomnia | 105 (23) | 5 (1) | 116 (25) | 10 (2)
Respiratory, Thoracic and Mediastinal Disorders
Dyspnea [Dyspnea includes dyspnea and dyspnea exertional.] | 128 (28) | 23 (5) | 69 (15) | 8 (2)
Cough [Cough includes cough and productive cough.] | 97 (21) | 0 (0) | 61 (13) | 2 (0)
Vascular Disorders
Hypertension [Hypertension includes hypertension, hypertensive crisis, and hypertensive emergency.] | 83 (18) | 30 (7) | 33 (7) | 12 (3)
Kd = Kyprolis and dexamethasone; Vd = bortezomib and dexamethasone

The event rate of ≥ Grade 2 peripheral neuropathy in the Kd arm was 7% (95% CI: 5, 9) versus 35% (95% CI: 31, 39) in the Vd arm.

Adverse Reactions Occurring at a Frequency of < 10%

- Blood and lymphatic system disorders: febrile neutropenia, leukopenia, lymphopenia, neutropenia, thrombotic microangiopathy, thrombotic thrombocytopenic purpura
- Cardiac disorders: atrial fibrillation, cardiac arrest, cardiac failure, cardiac failure congestive, myocardial infarction, myocardial ischemia, palpitations, tachycardia
- Ear and labyrinth disorders: tinnitus
- Eye disorders: cataract, vision blurred
- Gastrointestinal disorders: abdominal pain, abdominal pain upper, dyspepsia, gastrointestinal hemorrhage, toothache
- General disorders and administration site conditions: chest pain, chills, influenza like illness, infusion site reactions (including inflammation, pain, and erythema), malaise, pain
- Hepatobiliary disorders: cholestasis, hepatic failure, hyperbilirubinemia
- Immune system disorders: drug hypersensitivity
- Infections: bronchopneumonia, gastroenteritis, influenza, lung infection, nasopharyngitis, pneumonia, rhinitis, sepsis, urinary tract infection, viral infection
- Metabolism and nutrition disorders: decreased appetite, dehydration, hypercalcemia, hyperkalemia, hyperuricemia, hypoalbuminemia, hypocalcemia, hypomagnesemia, hyponatremia, hypophosphatemia, tumor lysis syndrome
- Musculoskeletal and connective tissue disorders: muscular weakness, musculoskeletal chest pain, musculoskeletal pain, myalgia
- Nervous system disorders: cerebrovascular accident, dizziness, hypoesthesia, paresthesia, posterior reversible encephalopathy syndrome
- Psychiatric disorders: anxiety
- Renal and urinary disorders: renal failure, renal failure acute, renal impairment
- Respiratory, thoracic and mediastinal disorders: acute respiratory distress syndrome, dysphonia, epistaxis, interstitial lung disease, oropharyngeal pain, pneumonitis, pulmonary embolism, pulmonary edema, pulmonary hypertension, wheezing
- Skin and subcutaneous tissue disorders: erythema, hyperhidrosis, pruritus, rash
- Vascular disorders: deep vein thrombosis, flushing, hypotension

Table 11 describes Grade 3–4 laboratory abnormalities reported at a rate of ≥ 10% in the Kd arm.

Table 11: Grade 3–4 Laboratory Abnormalities (≥ 10%) in Months 1–6 in Patients Who Received Kd (20/56 mg/m^2 Regimen) in ENDEAVOR
Laboratory Abnormality | Kd (N = 463) n (%) | Vd (N = 456) n (%)
Decreased lymphocytes | 249 (54) | 180 (40)
Increased uric acid | 244 (53) | 198 (43)
Decreased hemoglobin | 79 (17) | 68 (15)
Decreased platelets | 85 (18) | 77 (17)
Decreased phosphorus | 74 (16) | 61 (13)
Decreased creatinine clearance [Calculated using the Cockcroft-Gault formula.] | 65 (14) | 49 (11)
Increased potassium | 55 (12) | 21 (5)
Kd = Kyprolis and dexamethasone; Vd = bortezomib and dexamethasone

A.R.R.O.W.

The safety of Kyprolis in combination with dexamethasone was evaluated in A.R.R.O.W. [see Clinical Studies (14.2)]. Patients received treatment for a median duration of 38 weeks in the Kd 20/70 mg/m^2 arm once weekly and 29.1 weeks in the Kd 20/27 mg/m^2 twice weekly arm. The safety profile for the once weekly Kd 20/70 mg/m^2 regimen was similar to the twice weekly Kd 20/27 mg/m^2 regimen.

Deaths due to adverse reactions within 30 days of last study treatment occurred in 22/238 (9%) patients in the Kd 20/70 mg/m^2 arm and 18/235 (8%) patients in the Kd 20/27 mg/m^2 arm. The most frequent fatal adverse reactions occurring in patients (%) in the two arms (once weekly Kd 20/70 mg/m^2 versus twice weekly Kd 20/27 mg/m^2) were sepsis 2 (< 1%) versus 2 (< 1%), septic shock 2 (< 1%) versus 1 (< 1%), and infection 2 (< 1%) versus 0 (0%).

Serious adverse reactions were reported in 43% of the patients in the Kd 20/70 mg/m^2 arm and 41% of the patients in the Kd 20/27 mg/m^2 arm. In both arms, pneumonia was the most frequently reported serious adverse reaction (8% versus 7%).

Discontinuation due to any adverse reaction occurred in 13% in the Kd 20/70 mg/m^2 arm versus 12% in the Kd 20/27 mg/m^2 arm. The most frequent adverse reaction leading to discontinuation was acute kidney injury (2% versus 2%). The incidence of cardiac failure events was 3.8% in the once weekly Kd 20/70 mg/m^2 arm versus 5.1% in the twice weekly Kd 20/27 mg/m^2 arm.

Adverse reactions that occurred at a rate of 10% or greater in either Kd arm are presented in Table 12.

Table 12: Adverse Reactions in Patients Who Received Kd (≥ 10% in either Kd Arm) in A.R.R.O.W.
Adverse Reactions | Once weekly Kd 20/70 mg/m^2 (N = 238) n (%) |  | Twice weekly Kd 20/27 mg/m^2 (N = 235) n (%)
Adverse Reactions | Any Grade | Grade ≥ 3 | Any Grade | Grade ≥ 3
Blood and Lymphatic System Disorders
Anemia [Anemia includes anemia, hematocrit decreased, and hemoglobin decreased.] | 64 (27) | 42 (18) | 76 (32) | 42 (18)
Thrombocytopenia [Thrombocytopenia includes platelet count decreased and thrombocytopenia.] | 53 (22) | 26 (11) | 41 (17) | 27 (12)
Neutropenia [Neutropenia includes neutrophil count decreased and neutropenia.] | 30 (13) | 21 (9) | 27 (12) | 17 (7)
Gastrointestinal Disorders
Diarrhea | 44 (19) | 2 (1) | 47 (20) | 3 (1)
Nausea | 34 (14) | 1 (< 1) | 26 (11) | 2 (1)
General Disorders and Administration Site Conditions
Pyrexia | 55 (23) | 2 (1) | 38 (16) | 4 (2)
Fatigue | 48 (20) | 11 (5) | 47 (20) | 5 (2)
Asthenia | 24 (10) | 3 (1) | 25 (11) | 2 (1)
Peripheral edema | 18 (8) | 0 (0) | 25 (11) | 2 (1)
Infections
Respiratory tract infection [Respiratory tract infection includes respiratory tract infection, lower respiratory tract infection, upper respiratory tract infection, and viral upper respiratory tract infection.] | 70 (29) | 7 (3) | 79 (34) | 7 (3)
Pneumonia | 28 (12) | 24 (10) | 20 (9) | 16 (7)
Bronchitis | 27 (11) | 2 (1) | 25 (11) | 5 (2)
Musculoskeletal and Connective Tissue Disorders
Back pain | 28 (12) | 2 (1) | 28 (12) | 4 (2)
Nervous System Disorders
Headache | 25 (11) | 1 (< 1) | 23 (10) | 1 (< 1)
Psychiatric Disorders
Insomnia | 35 (15) | 2 (1) | 47 (20) | 0 (0)
Respiratory, Thoracic and Mediastinal Disorders
Cough [Cough includes cough and productive cough.] | 37 (16) | 2 (1) | 31 (13) | 0 (0)
Dyspnea [Dyspnea includes dyspnea and dyspnea exertional.] | 28 (12) | 1 (< 1) | 26 (11) | 2 (1)
Vascular Disorders
Hypertension [Hypertension includes hypertension and hypertensive crisis.] | 51 (21) | 13 (6) | 48 (20) | 12 (5)
Kd = Kyprolis and dexamethasone

Adverse Reactions Occurring at a Frequency of < 10%

- Blood and lymphatic system disorders: febrile neutropenia, leukopenia, lymphopenia, neutropenia, thrombotic microangiopathy
- Cardiac disorders: atrial fibrillation, cardiac arrest, cardiac failure, cardiac failure congestive, myocardial infarction, myocardial ischemia, palpitations, pericardial effusion, tachycardia
- Ear and labyrinth disorders: tinnitus
- Eye disorders: cataract, vision blurred
- Gastrointestinal disorders: abdominal pain, abdominal pain upper, constipation, dyspepsia, toothache, vomiting
- General disorders and administration site conditions: chest pain, chills, influenza like illness, infusion site reactions (including inflammation, pain, and erythema), malaise, pain
- Hepatobiliary disorders: cholestasis, hepatic failure, hyperbilirubinemia
- Infections: clostridium difficile colitis, gastroenteritis, influenza, lung infection, nasopharyngitis, rhinitis, sepsis, septic shock, urinary tract infection, viral infection
- Metabolism and nutrition disorders: decreased appetite, dehydration, hypercalcemia, hyperglycemia, hyperkalemia, hyperuricemia, hypoalbuminemia, hypocalcemia, hypomagnesemia, hyponatremia, hypophosphatemia, tumor lysis syndrome
- Musculoskeletal and connective tissue disorders: muscle spasms, muscular weakness, musculoskeletal chest pain, musculoskeletal pain, myalgia
- Nervous system disorders: cerebrovascular accident, dizziness, paresthesia, peripheral neuropathy
- Psychiatric disorders: anxiety, delirium
- Renal and urinary disorders: acute kidney injury, renal failure, renal impairment
- Respiratory, thoracic and mediastinal disorders: acute respiratory distress syndrome, dysphonia, epistaxis, interstitial lung disease, oropharyngeal pain, pneumonitis, pulmonary hemorrhage, pulmonary embolism, pulmonary hypertension, pulmonary edema, wheezing
- Skin and subcutaneous tissue disorders: erythema, hyperhidrosis, pruritus, rash
- Vascular disorders: deep vein thrombosis, flushing, hypotension

Kyprolis in Combination with Intravenous Daratumumab and Dexamethasone

The safety of Kyprolis in combination with intravenous daratumumab and dexamethasone was evaluated in two trials (CANDOR and EQUULEUS).

CANDOR

The safety of Kyprolis 20/56 mg/m^2 twice weekly in combination with intravenous daratumumab and dexamethasone (DKd) was evaluated in CANDOR [see Clinical Studies (14.3)]. Patients received Kyprolis for a median duration of 58 weeks in the DKd arm and 40 weeks in the Kd arm.

Serious adverse reactions were reported in 56% of the patients in the DKd arm and 46% of the patients in the Kd arm. The most frequent serious adverse reactions reported in the DKd arm as compared with the Kd arm were pneumonia (14% versus 9%), pyrexia (4.2% versus 2.0%), influenza (3.9% versus 1.3%), sepsis (3.9% versus 1.3%), anemia (2.3% versus 0.7%), bronchitis (1.9% versus 0%) and diarrhea (1.6% versus 0%). Fatal adverse reactions within 30 days of the last dose of any study treatment occurred in 10% of 308 patients in the DKd arm compared with 5% of 153 patients in the Kd arm. The most frequent fatal adverse reaction (DKd versus Kd) was infection 4.5% versus 2.6%.

Permanent discontinuation due to an adverse reaction in patients who received Kyprolis occurred in 21% of patients in the DKd arm versus 22% in the Kd arm. The most frequent adverse reactions leading to discontinuation of Kyprolis were cardiac failure (1.9%) and fatigue (1.9%) in the DKd arm and cardiac failure (2.0%), hypertension (2.0%) and acute kidney injury (2.0%) in the Kd arm. Interruption of Kyprolis due to adverse reactions occurred in 71% of patients in DKd arm versus 63% in the Kd arm. Dose reduction of Kyprolis due to adverse reactions occurred in 25% of patients in DKd arm versus 20% in the Kd arm.

Infusion-related reactions that occurred following the first Kyprolis dose was 13% in the DKd arm versus 1% in the Kd arm.

Table 13 summarizes the adverse reactions in CANDOR.

Table 13: Adverse Reactions (≥ 15%) in Patients Who Received either DKd or Kd (20/56 mg/m^2 Regimen) in CANDOR
Adverse Reactions | Twice weekly DKd (N = 308) |  | Twice weekly Kd (N = 153)
Adverse Reactions | All Grades (%) | Grade 3 or 4 (%) | All Grades (%) | Grade 3 or 4 (%)
General Disorders and Administration Site Conditions
Infusion-related reaction [The incidence of infusion related reactions is based on a group of symptoms (including hypertension, pyrexia, rash, myalgia, hypotension, blood pressure increased, urticaria, acute kidney injury, bronchospasm, face edema, hypersensitivity, syncope, wheezing, eye pruritus, eyelid edema, renal failure, swelling face) related to infusion reactions which occurred within 1 day after DKd or Kd administration.] | 41 | 12 | 28 | 5
Fatigue [Fatigue includes fatigue and asthenia.] | 32 | 11 | 28 | 8
Pyrexia | 20 | 1.9 | 15 | 0.7
Infections
Respiratory tract infection [Respiratory tract infection includes respiratory tract infection, lower respiratory tract infection, upper respiratory tract infection and viral upper respiratory tract infection.] | 40 [Includes fatal adverse reactions.] | 7 | 29 | 3.3
Pneumonia | 18 | 13 | 12 | 9
Bronchitis | 17 | 2.6 | 12 | 1.3
Blood and Lymphatic System Disorders
Thrombocytopenia [Thrombocytopenia includes platelet count decreased and thrombocytopenia.] | 37 | 25 | 30 | 16
Anemia [Anemia includes anemia, hematocrit decreased and hemoglobin decreased.] | 33 | 17 | 31 | 14
Gastrointestinal Disorders
Diarrhea | 32 | 3.9 | 14 | 0.7
Nausea | 18 | 0 | 13 | 0.7
Vascular Disorders
Hypertension | 31 | 18 | 28 | 13
Respiratory, Thoracic and Mediastinal Disorders
Cough [Cough includes productive cough and cough.] | 21 | 0 | 21 | 0
Dyspnea | 20 | 3.9 | 22 | 2.6
Psychiatric Disorders
Insomnia | 18 | 3.9 | 11 | 2.0
Musculoskeletal and Connective Tissue Disorders
Back pain | 16 | 1.9 | 10 | 1.3
DKd = Kyprolis, daratumumab, and dexamethasone; Kd = Kyprolis and dexamethasone

Adverse Reactions Occurring at a Frequency of < 15%

- Blood and lymphatic system disorders: febrile neutropenia, thrombotic thrombocytopenic purpura
- Cardiac disorders: atrial fibrillation, cardiac arrest, cardiac failure, cardiomyopathy, myocardial infarction, myocardial ischemia, tachycardia
- Eye disorders: cataract
- Gastrointestinal disorders: abdominal pain, gastrointestinal hemorrhage
- General disorders and administration site conditions: chest pain, malaise
- Infections: gastroenteritis, influenza, lung infection, nasopharyngitis, sepsis, septic shock, urinary tract infection, viral infection
- Investigations: alanine aminotransferase increased, blood creatinine increased, C-reactive protein increased, ejection fraction decreased
- Metabolism and nutrition disorders: dehydration, hyperglycemia, hyperkalemia, hypokalemia, hyponatremia, tumor lysis syndrome
- Musculoskeletal and connective tissue disorders: pain in extremity
- Nervous system disorders: cerebrovascular accident, intracranial hemorrhage, posterior reversible encephalopathy syndrome, peripheral neuropathy
- Psychiatric disorders: anxiety
- Renal and urinary disorders: acute kidney injury, renal failure, renal impairment
- Respiratory, thoracic and mediastinal disorders: acute respiratory failure, epistaxis, interstitial lung disease, pneumonitis, pulmonary embolism, pulmonary hypertension, pulmonary edema
- Skin and subcutaneous tissue disorders: rash
- Vascular disorders: deep vein thrombosis, hypertensive crisis

EQUULEUS

The safety of Kyprolis 20/70 mg/m^2 once weekly in combination with intravenous daratumumab and dexamethasone (DKd) was evaluated in EQUULEUS [see Clinical Studies (14.3)]. Patients received Kyprolis for a median duration of 66 weeks.

Serious adverse reactions were reported in 48% of patients. The most frequent serious adverse reactions reported were pneumonia (4.7%), upper respiratory tract infection (4.7%), basal cell carcinoma (4.7%), influenza (3.5%), general physical health deterioration (3.5%) and hypercalcemia (3.5%). Fatal adverse reactions within 30 days of the last dose of any study treatment occurred in 3.5% of patients who died of general physical health deterioration, multi-organ failure secondary to pulmonary aspergillosis, and disease progression.

Discontinuation of Kyprolis occurred in 19% of patients. The most frequent adverse reaction leading to discontinuation was asthenia (2%). Interruption of Kyprolis due to adverse reactions occurred in 77% of patients. Dose reduction of Kyprolis due to adverse reactions occurred in 31% of patients in DKd.

Infusion-related reactions that occurred following the first Kyprolis dose was 11%. Pulmonary hypertension adverse reactions were reported in 4.7% of patients in EQUULEUS.

Table 14 summarizes the adverse reactions in EQUULEUS.

Table 14: Adverse Reactions (≥ 15%) in Patients Who Received DKd (20/70 mg/m^2 Regimen) in EQUULEUS
Adverse Reactions | Once weekly DKd (N = 85)
Adverse Reactions | All Grades (%) | Grade 3 or 4 (%)
Blood and Lymphatic System Disorders
Thrombocytopenia [Thrombocytopenia includes platelet count decreased and thrombocytopenia.] | 68 | 32
Anemia [Anemia includes anemia, hematocrit decreased and hemoglobin decreased.] | 52 | 21
Neutropenia [Neutropenia includes neutrophil count decreased and neutropenia.] | 31 | 21
Lymphopenia [Lymphopenia includes lymphocyte count decreased and lymphopenia.] | 29 | 25
General Disorders and Administration Site Conditions
Fatigue [Fatigue includes fatigue and asthenia.] | 54 | 18
Infusion-related reaction [The incidence of infusion related reactions is based on a group of symptoms (including hypertension, pyrexia, rash, myalgia, hypotension, blood pressure increased, urticaria, acute kidney injury, bronchospasm, face edema, hypersensitivity, syncope, wheezing, eye pruritus, eyelid edema, renal failure, swelling face) related to infusion reactions which occurred within 1 day after DKd administration.] | 53 | 12
Pyrexia | 37 | 1.2
Infections
Respiratory tract infection [Respiratory tract infection includes respiratory tract infection, lower respiratory tract infection, upper respiratory tract infection and viral upper respiratory tract infection.] | 53 | 3.5
Bronchitis | 19 | 0
Nasopharyngitis | 18 | 0
Influenza | 17 | 3.5
Gastrointestinal Disorders
Nausea | 42 | 1.2
Vomiting | 40 | 1.2
Diarrhea | 38 | 2.4
Constipation | 17 | 0
Respiratory, Thoracic and Mediastinal Disorders
Dyspnea | 35 | 3.5
Cough [Cough includes productive cough and cough.] | 33 | 0
Vascular Disorders
Hypertension | 33 | 20
Psychiatric Disorders
Insomnia | 33 | 4.7
Nervous System Disorders
Headache | 27 | 1.2
Musculoskeletal and Connective Tissue Disorders
Back pain | 25 | 0
Pain in extremity | 15 | 0
DKd = Kyprolis, daratumumab, and dexamethasone; Kd = Kyprolis and dexamethasone

Adverse Reactions Occurring at a Frequency of < 15%

- Blood and lymphatic system disorders: febrile neutropenia, thrombotic microangiopathy
- Cardiac disorders: cardiac failure, myocardial ischemia
- Gastrointestinal disorders: abdominal pain
- General disorders and administration site conditions: multiple organ dysfunction syndrome
- Infections: pneumonia, sepsis, septic shock
- Metabolism and nutrition disorders: dehydration, hypercalcemia
- Renal and urinary disorders: acute kidney injury, renal failure, renal impairment
- Respiratory, thoracic and mediastinal disorders: pulmonary embolism, pulmonary hypertension
- Vascular disorders: hypotension

Kyprolis in Combination with Subcutaneous Daratumumab and Dexamethasone

The safety of Kyprolis in combination with daratumumab and hyaluronidase-fihj and dexamethasone was evaluated in PLEIADES [see Clinical Studies (14.3)].

PLEIADES

The safety of Kyprolis in combination with daratumumab and hyaluronidase-fihj and dexamethasone (DKd) was evaluated in a single-arm cohort of PLEIADES. Patients received Kyprolis as a 30-minute IV infusion once weekly for three weeks (Days 1, 8, and 15), followed by a 13-day rest period (Days 16 to 28) and continued until disease progression or unacceptable toxicity (N=66) in combination with daratumumab and hyaluronidase-fihj and dexamethasone. Among these patients, 77% were exposed for 6 months or longer and 27% were exposed for greater than one year.

Serious adverse reactions occurred in 27% of patients who received Kyprolis in combination with daratumumab and hyaluronidase-fihj and dexamethasone. Fatal adverse reactions occurred in 3% of patients who received Kyprolis in combination with daratumumab and hyaluronidase-fihj and dexamethasone.

Permanent discontinuation of Kyprolis due to an adverse reaction occurred in 6% of patients who received Kyprolis.

Dosage interruptions due to an adverse reaction occurred in 46% of patients who received Kyprolis.

The most common adverse reactions (≥20%) were upper respiratory tract infection, fatigue, insomnia, hypertension, diarrhea, cough, dyspnea, headache, pyrexia, nausea and edema peripheral.

Table 15 summarizes the adverse reactions in patients who received Kyprolis with subcutaneous daratumumab and dexamethasone (DKd) in PLEIADES.

Table 15: Adverse Reactions (≥10%) in Patients Who Received Kyprolis with Subcutaneous Daratumumab and Dexamethasone (DKd) in PLEIADES
Adverse Reaction | DKd (N=66)
Adverse Reaction | All Grades (%) | Grade ≥3 (%)
Infections and infestations
Upper respiratory tract infection [Upper respiratory tract infection includes nasopharyngitis, pharyngitis, respiratory tract infection, respiratory tract infection viral, rhinitis, sinusitis, tonsillitis, upper respiratory tract infection, viral pharyngitis, and viral upper respiratory tract infection.] | 52 | 0
Bronchitis [Bronchitis includes bronchitis, and bronchitis viral.] | 12 | 2 [Only Grade 3 adverse reactions occurred.]
General disorders and administration site conditions
Fatigue [Fatigue includes asthenia, and fatigue.] | 39 | 2
Pyrexia | 21 | 2
Edema peripheral [Edema peripheral includes generalized edema, edema peripheral, and peripheral swelling.] | 20 | 0
Psychiatric disorders
Insomnia | 33 | 6
Vascular disorders
Hypertension [Hypertension includes blood pressure increased, and hypertension.] | 32 | 21
Gastrointestinal disorders
Diarrhea | 29 | 0
Nausea | 21 | 0
Vomiting | 15 | 0
Respiratory, thoracic and mediastinal disorders
Cough [Cough includes cough, and productive cough.] | 24 | 0
Dyspnea [Dyspnea includes dyspnea, and dyspnea exertional.] | 23 | 2
Nervous system disorders
Headache | 23 | 0
Peripheral sensory neuropathy | 11 | 0
Musculoskeletal and connective tissue disorders
Back pain | 17 | 2
Musculoskeletal chest pain | 11 | 0

Clinically relevant adverse reactions in <10% of patients who received Kyprolis with subcutaneous daratumumab and dexamethasone include:

- Gastrointestinal disorders: abdominal pain, constipation, pancreatitis
- Infection and infestations: pneumonia, influenza, urinary tract infection, herpes zoster, sepsis
- Metabolism and nutrition disorders: hyperglycemia, decreased appetite, hypocalcemia
- Musculoskeletal and connective tissue disorders: muscle spasms, arthralgia
- Nervous system disorders: paresthesia, dizziness, syncope
- General disorders and administration site conditions: injection site reaction, infusion reactions, chills
- Skin and subcutaneous tissue disorders: rash, pruritus
- Cardiac disorders: cardiac failure
- Vascular disorders: hypotension

Table 16 summarizes the laboratory abnormalities in patients who received Kyprolis with subcutaneous daratumumab and dexamethasone in PLEIADES.

Table 16: Select Laboratory Abnormalities (≥30%) Worsening from Baseline in Patients Who Received DKd in PLEIADES
Laboratory Abnormality | DKd [Denominator is based on the safety population treated with DKd (N=66).]
Laboratory Abnormality | All Grades (%) | Grades 3-4 (%)
Decreased platelets | 88 | 18
Decreased lymphocytes | 83 | 50
Decreased leukocytes | 68 | 18
Decreased neutrophils | 55 | 15
Decreased hemoglobin | 47 | 6
Decreased corrected calcium | 45 | 2
Increased alanine aminotransferase (ALT) | 35 | 5

Kyprolis in Combination with Isatuximab and Dexamethasone

The safety of Kyprolis in combination with isatuximab and dexamethasone was evaluated in IKEMA, a randomized, open-label clinical trial in patients with previously treated multiple myeloma [see Clinical Studies (14.4)]. Patients received Kyprolis 20/56 mg/m^2 twice weekly in combination with isatuximab and dexamethasone (Isa-Kd) (n=177) or Kyprolis and dexamethasone (Kd) (n=122). Among patients receiving Isa-Kd, the median exposure to Kyprolis was 65 weeks.

Serious adverse reactions occurred in 59% of patients receiving Isa-Kd. The most frequent serious adverse reactions in >5% of patients who received Isa-Kd were pneumonia (25%) and upper respiratory tract infections (9%). Adverse reactions with a fatal outcome during treatment were reported in 3.4% of patients in the Isa-Kd group (those occurring in more than 1% of patients were pneumonia occurring in 1.7% and cardiac failure in 1.1% of patients).

Permanent treatment discontinuation due to an adverse reaction (grades 1-4) occurred in 8% of patients who received Isa-Kd. The most frequent adverse reactions requiring permanent discontinuation in patients who received Isa-Kd were infections (2.8%).

Dosage interruptions due to an adverse reaction occurred in 4% of patients who received Kyprolis in the Isa-Kd group. The most frequent adverse reactions requiring dosage interruption in patients who received Kyprolis in the Isa-Kd group were administration site extravasation (1.1%) and infusion site extravasation (1.1%).

Dose reductions or omissions of Kyprolis due to an adverse reaction in the Isa-Kd group occurred in 67% of patients. Adverse reactions which required dose reductions or omissions in >10% of patients who received Kyprolis in the Isa-Kd group were upper respiratory tract infection (12.4%) and hypertension (11.9%).

The most common adverse reactions (≥20%) were upper respiratory tract infection, infusion-related reactions, fatigue, hypertension, diarrhea, pneumonia, dyspnea, insomnia, bronchitis, cough and back pain.

Table 17 summarizes the adverse reactions in IKEMA.

Table 17: Adverse Reactions (≥10%) in Patients Who Received Kyprolis with Isatuximab and Dexamethasone (Isa-Kd) in IKEMA
Adverse Reactions | Isa-Kd (N = 177) |  | Kd (N = 122)
Adverse Reactions | All Grades (%) | Grade 3 or 4 (%) | All Grades (%) | Grade 3 or 4 (%)
Infections
Upper respiratory tract infection [Upper respiratory tract infection includes acute sinusitis, chronic sinusitis, H1N1 influenza, H3N2 influenza, influenza, laryngitis, laryngitis viral, nasal herpes, nasopharyngitis, pharyngitis, pharyngotonsillitis, respiratory syncytial virus infection, rhinitis, sinusitis, sinusitis bacterial, tonsillitis, tracheitis, upper respiratory tract infection, viral rhinitis, respiratory tract infection, respiratory tract infection viral, influenza like illness, parainfluenzae virus infection, respiratory tract infection bacterial, and viral upper respiratory tract infection.] | 67 | 9 | 57 | 7
Pneumonia [Pneumonia includes atypical pneumonia, lower respiratory tract infection, lower respiratory tract infection viral, pneumocystis jirovecii pneumonia, pneumonia, pneumonia influenzal, pneumonia legionella, pneumonia pneumococcal, pneumonia respiratory syncytial viral, pneumonia streptococcal, pneumonia viral, pulmonary sepsis, and pulmonary tuberculosis.] | 36 | 22 | 30 | 18
Bronchitis [Bronchitis includes bronchitis, bronchitis viral, respiratory syncytial virus bronchitis, bronchitis chronic, and tracheobronchitis.] | 24 | 2.3 | 13 | 0.8
General Disorders and Administration Site Conditions
Infusion-related reaction [Infusion-related reaction includes infusion-related reaction, cytokine release syndrome, and hypersensitivity.] | 46 | 0.6 | 3.3 | 0
Fatigue [Fatigue includes fatigue and asthenia.] | 42 | 5 | 32 | 3.3
Vascular Disorders
Hypertension [Hypertension includes hypertension, blood pressure increased, and hypertensive crisis.] | 37 | 21 | 32 | 20
Gastrointestinal Disorders
Diarrhea | 36 | 2.8 | 29 | 2.5
Vomiting | 15 | 1.1 | 9 | 0.8
Respiratory, Thoracic and Mediastinal Disorders
Dyspnea [Dyspnea includes dyspnea and dyspnea exertional.] | 29 | 5 | 24 | 0.8
Cough [Cough includes cough, productive cough, and allergic cough.] | 23 | 0 | 15 | 0
Isa-Kd = Kyprolis, isatuximab, and dexamethasone

Table 18 summarizes the laboratory abnormalities in patients who received Kyprolis with isatuximab and dexamethasone versus Kyprolis with dexamethasone in IKEMA.

Table 18: Hematology Laboratory Abnormalities During the Treatment Period in Patients Who Received Isa-Kd versus Kd in IKEMA
Laboratory Abnormality | Isa-Kd [Denominator is based on the safety population.] (N=177) |  | Kd (N=122)
Laboratory Abnormality | All Grades (%) | Grades 3-4 (%) | All Grades (%) | Grades 3-4 (%)
Hemoglobin decreased | 99 | 22 | 99 | 20
Lymphocytes decreased | 94 | 69 | 95 | 57
Platelets decreased | 94 | 30 | 88 | 24
Neutrophils decreased | 55 | 20 | 43 | 8

Kyprolis in Patients who Received Monotherapy

The safety of Kyprolis 20/27 mg/m^2 as a 10-minute infusion was evaluated in clinical trials consisting of 598 patients with relapsed and/or refractory myeloma [see Clinical Studies (14.5)]. Premedication with dexamethasone 4 mg was required before each dose in Cycle 1 and was optional for subsequent cycles. The median age was 64 years (range 32–87), and approximately 57% were male. The patients received a median of 5 (range 1–20) prior regimens. The median number of cycles initiated was 4 (range 1–35).

Deaths due to adverse reactions within 30 days of the last dose of Kyprolis occurred in 30/598 (5%) patients receiving Kyprolis monotherapy. These adverse reactions were related to cardiac disorders in 10 (2%) patients, infections in 8 (1%) patients, renal disorders in 4 (< 1%) patients, and other adverse reactions in 8 (1%) patients.

Serious adverse reactions were reported in 50% of patients in the pooled Kyprolis monotherapy studies (N = 598). The most frequent serious adverse reactions were: pneumonia (8%), acute renal failure (5%), disease progression (4%), pyrexia (3%), hypercalcemia (3%), congestive heart failure (3%), multiple myeloma (3%), anemia (2%), and dyspnea (2%).

In FOCUS, a randomized trial comparing Kyprolis as a single agent versus corticosteroids with optional oral cyclophosphamide for patients with relapsed and refractory multiple myeloma, mortality was higher in the patients treated with Kyprolis in comparison to the control arm in the subgroup of 48 patients ≥ 75 years of age. The most common cause of discontinuation due to an adverse reaction was acute renal failure (2%).

Safety of Kyprolis monotherapy dosed at 20/56 mg/m^2 by 30-minute infusion was evaluated in a multicenter, open-label study in patients with relapsed and/or refractory multiple myeloma [see Clinical Studies (14.5)]. The patients received a median of 4 (range 1–10) prior regimens.

Adverse reactions occurring with Kyprolis monotherapy are presented in Table 19.

Table 19: Adverse Reactions (≥ 20%) with Kyprolis Monotherapy
Adverse Reactions | 20/56 mg/m^2 by 30-minute infusion (N = 24) |  | 20/27 mg/m^2 by 2- to 10-minute infusion (N = 598)
Adverse Reactions | All Grades n (%) | Grades 3-5 n (%) | All Grades n (%) | Grades 3-5 n (%)
Fatigue | 14 (58) | 2 (8) | 238 (40) | 25 (4)
Dyspnea [Dyspnea includes dyspnea and dyspnea exertional.] | 14 (58) | 2 (8) | 202 (34) | 21 (4)
Pyrexia | 14 (58) | 0 | 177 (30) | 11 (2)
Thrombocytopenia | 13 (54) | 13 (54) | 220 (37) | 152 (25)
Nausea | 13 (54) | 0 | 211 (35) | 7 (1)
Anemia | 10 (42) | 7 (29) | 291 (49) | 141 (24)
Hypertension [Hypertension includes hypertension, hypertensive crisis, and hypertensive emergency.] | 10 (42) | 3 (13) | 90 (15) | 22 (4)
Chills | 9 (38) | 0 | 73 (12) | 1 (< 1)
Headache | 8 (33) | 0 | 141 (24) | 7 (1)
Cough [Cough includes cough and productive cough.] | 8 (33) | 0 | 134 (22) | 2 (< 1)
Vomiting | 8 (33) | 0 | 104 (17) | 4 (1)
Lymphopenia | 8 (33) | 8 (33) | 85 (14) | 73 (12)
Insomnia | 7 (29) | 0 | 75 (13) | 0
Dizziness | 7 (29) | 0 | 64 (11) | 5 (1)
Diarrhea | 6 (25) | 1 (4) | 160 (27) | 8 (1)
Blood creatinine increased | 6 (25) | 1 (4) | 103 (17) | 15 (3)
Peripheral edema | 5 (21) | 0 | 118 (20) | 1 (< 1)
Back pain | 5 (21) | 1 (4) | 115 (19) | 19 (3)
Upper respiratory tract infection | 5 (21) | 1 (4) | 112 (19) | 15 (3)
Decreased appetite | 5 (21) | 0 | 89 (15) | 2 (< 1)
Muscle spasms | 5 (21) | 0 | 62 (10) | 2 (< 1)
Chest pain | 5 (21) | 0 | 20 (3) | 1 (< 1)

Adverse Reactions Occurring at a Frequency of < 20%

- Blood and lymphatic system disorders: febrile neutropenia, leukopenia, neutropenia
- Cardiac disorders: cardiac arrest, cardiac failure, cardiac failure congestive, myocardial infarction, myocardial ischemia
- Ear and labyrinth disorders: tinnitus
- Eye disorders: cataract, blurred vision
- Gastrointestinal disorders: abdominal pain, abdominal pain upper, constipation, dyspepsia, gastrointestinal hemorrhage, toothache
- General disorders and administration site conditions: asthenia, infusion site reaction, multi-organ failure, pain
- Hepatobiliary disorders: hepatic failure
- Infections: bronchitis, bronchopneumonia, influenza, lung infection, pneumonia, nasopharyngitis, respiratory tract infection, rhinitis, sepsis, urinary tract infection
- Metabolism and nutrition disorders: hypercalcemia, hyperglycemia, hyperkalemia, hyperuricemia, hypoalbuminemia, hypocalcemia, hypokalemia, hypomagnesemia, hyponatremia, hypophosphatemia, tumor lysis syndrome
- Musculoskeletal and connective tissue disorders: arthralgia, musculoskeletal pain, musculoskeletal chest pain, myalgia, pain in extremity
- Nervous system disorders: hypoesthesia, intracranial hemorrhage, paresthesia, peripheral motor neuropathy, peripheral neuropathy, peripheral sensory neuropathy
- Psychiatric disorders: anxiety
- Renal and urinary disorders: acute renal failure, renal failure, renal impairment
- Respiratory, thoracic and mediastinal disorders: dysphonia, epistaxis, oropharyngeal pain, pulmonary edema, pulmonary hemorrhage
- Skin and subcutaneous tissue disorders: erythema, hyperhidrosis, pruritus, rash
- Vascular disorders: embolic and thrombotic events, venous (including deep vein thrombosis and pulmonary embolism), hemorrhage, hypotension

Grade 3 and higher adverse reactions occurring at an incidence of > 1% include febrile neutropenia, cardiac arrest, cardiac failure congestive, pain, sepsis, urinary tract infection, hyperglycemia, hyperkalemia, hyperuricemia, hypoalbuminemia, hypocalcemia, hyponatremia, hypophosphatemia, renal failure, renal failure acute, renal impairment, pulmonary edema, and hypotension.

Table 20 describes Grade 3–4 laboratory abnormalities reported at a rate of > 10% for patients who received Kyprolis monotherapy.

Table 20: Grade 3–4 Laboratory Abnormalities (> 10%) with Kyprolis Monotherapy
Laboratory Abnormality | Kyprolis 20/56 mg/m^2 (N = 24) | Kyprolis 20/27 mg/m^2 (N = 598)
Decreased lymphocytes | 15 (63) | 151 (25)
Decreased platelets | 11 (46) | 184 (31)
Decreased hemoglobin | 7 (29) | 132 (22)
Decreased total white blood cell count | 3 (13) | 71 (12)
Decreased sodium | 2 (8) | 69 (12)
Decreased absolute neutrophil count | 2 (8) | 67 (11)

6.2 Postmarketing Experience

The following adverse reactions have been identified during postapproval use of Kyprolis. Because these reactions are reported voluntarily from a population of uncertain size, it is not always possible to reliably estimate their frequency or establish a causal relationship to drug exposure: hemolytic uremic syndrome (HUS), hepatitis B virus reactivation, gastrointestinal perforation, pericarditis, and cytomegalovirus infection, including chorioretinitis, pneumonitis, enterocolitis, viremia, intestinal obstruction, and acute pancreatitis.

8 USE IN SPECIFIC POPULATIONS

8.1 Pregnancy

Risk Summary

Kyprolis can cause fetal harm based on findings from animal studies and its mechanism of action [see Clinical Pharmacology (12.1)]. There are no available data on Kyprolis use in pregnant women to evaluate for drug-associated risks. Kyprolis caused embryo-fetal lethality in rabbits at doses lower than the clinical dose (see Data). Advise pregnant women of the potential risk to the fetus.

In the U.S. general population, the estimated background risk of major birth defects and miscarriage in clinically recognized pregnancies is 2%–4% and 15%–20%, respectively.

Data

Animal Data

Carfilzomib administered intravenously to pregnant rats and rabbits during the period of organogenesis was not teratogenic at doses up to 2 mg/kg/day in rats and 0.8 mg/kg/day in rabbits. In rabbits, there was an increase in pre-implantation loss at ≥ 0.4 mg/kg/day and an increase in early resorptions and post-implantation loss and a decrease in fetal weight at the maternally toxic dose of 0.8 mg/kg/day. The doses of 0.4 and 0.8 mg/kg/day in rabbits are approximately 20% and 40%, respectively, of the recommended dose in humans of 27 mg/m^2 based on BSA.

8.2 Lactation

Risk Summary

There are no data on the presence of Kyprolis in human milk, the effects on the breastfed child, or the effects of the drug on milk production. Because of the potential for serious adverse reactions in the breastfed child, advise women not to breastfeed during treatment with Kyprolis and for 2 weeks after treatment.

8.3 Females and Males of Reproductive Potential

Based on its mechanism of action and findings in animals, Kyprolis can cause fetal harm when administered to a pregnant woman [see Use in Specific Populations (8.1)].

Pregnancy Testing

Conduct pregnancy testing on females of reproductive potential prior to initiating Kyprolis treatment.

Contraception

Females

Advise females of reproductive potential to use effective contraception during treatment with Kyprolis and for 6 months following the last dose.

Males

Advise males with female sexual partners of reproductive potential to use effective contraception during treatment with Kyprolis and for 3 months following the last dose.

Infertility

Based on the mechanism of action, Kyprolis may have an effect on either male or female fertility [see Clinical Pharmacology (12.1), Nonclinical Toxicology (13.1)]. There are no data on the effect of Kyprolis on human fertility.

8.4 Pediatric Use

The safety and effectiveness of Kyprolis in pediatric patients have not been established.

The safety and effectiveness of Kyprolis in combination with chemotherapy was evaluated, but not established in an open label trial (Study 20140106; NCT02303821) in 124 patients aged 1 to younger than 17 years with relapsed or refractory B-cell acute lymphoblastic leukemia (ALL) who have received prior targeted B-cell immune therapy or relapsed or refractory T-cell ALL.

No new safety signals were observed in these pediatric patients. The systemic exposure of carfilzomib in these pediatric patients was within range of that observed in adults given the same dose based on body surface area.

8.5 Geriatric Use

Of the 2,837 patients with relapsed or refractory multiple myeloma exposed to Kyprolis in monotherapy and combination therapy studies [see Clinical Studies (14.1, 14.2, 14.3, 14.4, 14.5)], 50% were 65 years and older, while 13% were 75 years and older. The incidence of serious adverse reactions was 50% in patients < 65 years of age, 60% in patients 65 to 74 years of age, and 63% in patients ≥ 75 years of age. Of the 308 patients in CANDOR who received DKd, 47% of patients were 65 years and older, while 9% were 75 years and older. Fatal adverse reactions in the DKd arm of CANDOR occurred in 6% of patients < 65 years of age, 14% of patients between 65 to 74 years of age, and 14% of patients ≥ 75 years of age [see Adverse Reactions (6.1)]. No overall differences in effectiveness were observed between older and younger patients.

8.6 Hepatic Impairment

Reduce the dose of Kyprolis by 25% in patients with mild (total bilirubin 1 to 1.5 × ULN and any AST or total bilirubin ≤ ULN and AST > ULN) or moderate (total bilirubin > 1.5 to 3 × ULN and any AST) hepatic impairment. A recommended dosage of Kyprolis has not been established for patients with severe hepatic impairment (total bilirubin > 3 × ULN and any AST) [see Dosage and Administration (2.4), Clinical Pharmacology (12.3)].

The incidence of serious adverse reactions was higher in patients with mild, moderate, and severe hepatic impairment combined (22/35 or 63%) than in patients with normal hepatic function (3/11 or 27%) [see Warnings and Precautions (5.12), Clinical Pharmacology (12.3)].

10 OVERDOSAGE

Acute onset of chills, hypotension, renal insufficiency, thrombocytopenia, and lymphopenia has been reported following a dose of 200 mg of Kyprolis administered in error.

There is no known specific antidote for Kyprolis overdosage. In the event of overdose, monitor patients for adverse reactions and provide supportive care as appropriate.

11 DESCRIPTION

Carfilzomib is a proteasome inhibitor. The chemical name for carfilzomib is (2S)-N-((S)-1-((S)-4-methyl-1-((R)-2-methyloxiran-2-yl)-1-oxopentan-2-ylcarbamoyl)-2-phenylethyl)-2-((S)-2-(2-morpholinoacetamido)-4-phenylbutanamido)-4-methylpentanamide. Carfilzomib has the following structure:

Carfilzomib is a crystalline substance with a molecular weight of 719.9. The molecular formula is C40H57N5O7. Carfilzomib is practically insoluble in water and very slightly soluble in acidic conditions.

Kyprolis for injection, for intravenous use is a sterile, white to off-white lyophilized powder in a single-dose vial. Each 10 mg vial contains 10 mg of carfilzomib, 500 mg sulfobutylether beta-cyclodextrin, and 9.6 mg anhydrous citric acid and sodium hydroxide for pH adjustment (target pH 3.5). Each 30 mg vial contains 30 mg of carfilzomib, 1500 mg sulfobutylether beta-cyclodextrin, and 28.8 mg anhydrous citric acid and sodium hydroxide for pH adjustment (target pH 3.5). Each 60 mg vial contains 60 mg of carfilzomib, 3000 mg sulfobutylether beta-cyclodextrin, 57.7 mg citric acid, and sodium hydroxide for pH adjustment (target pH 3.5).

12 CLINICAL PHARMACOLOGY

12.1 Mechanism of Action

Carfilzomib is a tetrapeptide epoxyketone proteasome inhibitor that irreversibly binds to the N-terminal threonine-containing active sites of the 20S proteasome, the proteolytic core particle within the 26S proteasome. Carfilzomib had antiproliferative and proapoptotic activities in vitro in solid and hematologic tumor cells. In animals, carfilzomib inhibited proteasome activity in blood and tissue and delayed tumor growth in models of multiple myeloma, hematologic, and solid tumors.

12.2 Pharmacodynamics

Intravenous carfilzomib administration resulted in suppression of proteasome chymotrypsin-like (CT-L) activity when measured in blood 1 hour after the first dose. Doses of carfilzomib ≥ 15 mg/m^2 with or without lenalidomide and dexamethasone induced a ≥ 80% inhibition of the CT-L activity of the proteasome. In addition, carfilzomib, 20 mg/m^2 intravenously as a single agent, resulted in a mean inhibition of the low molecular mass polypeptide 2 (LMP2) and multicatalytic endopeptidase complex-like 1 (MECL1) subunits of the proteasome ranging from 26% to 32% and 41% to 49%, respectively. Proteasome inhibition was maintained for ≥ 48 hours following the first dose of carfilzomib for each week of dosing.

12.3 Pharmacokinetics

Carfilzomib at doses between 20 mg/m^2 and 70 mg/m^2 administered as a 30-minute infusion resulted in dose-dependent increases in maximum plasma concentrations (Cmax) and area under the curve over time to infinity (AUC0-INF) in patients with multiple myeloma. A dose-dependent increase in Cmax and AUC0-INF was also observed between carfilzomib 20 mg/m^2 and 56 mg/m^2 as a 2- to 10-minute infusion in patients with relapsed or refractory multiple myeloma. A 30-minute infusion resulted in a similar AUC0-INF, but 2- to 3-fold lower Cmax than that observed with a 2- to 10-minute infusion at the same dose. There was no evidence of carfilzomib accumulation following repeated administration of carfilzomib 70 mg/m^2 as a 30-minute once weekly infusion or 15 and 20 mg/m^2 as a 2- to 10-minute twice weekly infusion.

Table 21 lists the estimated mean average daily area under the curve in the first cycle (AUCC1,avg), average daily area under the curve at steady-state (AUCss) and Cmax at the highest dose in the first cycle (Cmax,C1) for the different dosing regimens.

Table 21: Carfilzomib Exposure Parameters for Different Dosing Regimens
Estimated Parameters (%CV) | 20/27 mg/m^2 twice weekly with 2- to 10-minute infusion | 20/56 mg/m^2 twice weekly with 30-minute infusion | 20/70 mg/m^2 once weekly with 30-minute infusion
AUCC1,avg (ng∙hr/mL) | 95 (40) | 170 (35) | 114 (36)
AUCss (ng∙hr/mL) | 111 (34) | 228 (28) | 150 (35)
Cmax,C1 (ng/mL) | 1282 (17) | 1166 (29) | 1595 (36)
CV = Coefficient of variation

Distribution

The mean steady-state volume of distribution of a 20 mg/m^2 dose of carfilzomib was 28 L. Carfilzomib is 97% bound to human plasma proteins over the concentration range of 0.4 to 4 micromolar in vitro.

Elimination

Carfilzomib has a half-life of ≤ 1 hour on Day 1 of Cycle 1 following intravenous doses ≥ 15 mg/m^2. The half-life was similar when administered either as a 30-minute infusion or a 2- to 10-minute infusion. The systemic clearance ranged from 151 to 263 L/hour.

Metabolism

Carfilzomib is rapidly metabolized. Peptidase cleavage and epoxide hydrolysis were the principal pathways of metabolism. Cytochrome P450 (CYP)-mediated mechanisms contribute a minor role in overall carfilzomib metabolism.

Excretion

Approximately 25% of the administered dose of carfilzomib was excreted in urine as metabolites in 24 hours. Urinary and fecal excretion of the parent compound was negligible (0.3% of total dose).

Specific Populations

Age (35-89 years), sex, race or ethnicity (80% White, 11% Black, 6% Asians, 3% Hispanics), and mild to severe renal impairment (creatinine clearance 15-89 mL/min) did not have clinically meaningful effects on the pharmacokinetics of carfilzomib.

Patients with Hepatic Impairment

Compared to patients with normal hepatic function, patients with mild (total bilirubin 1 to 1.5 × ULN and any AST or total bilirubin ≤ ULN and AST > ULN) and moderate (total bilirubin > 1.5 to 3 × ULN and any AST) hepatic impairment had approximately 50% higher carfilzomib AUC. The pharmacokinetics of carfilzomib has not been evaluated in patients with severe hepatic impairment (total bilirubin > 3 × ULN and any AST).

Patients with Renal Impairment

Relative to patients with normal renal function, ESRD patients on hemodialysis showed 33% higher carfilzomib AUC. Since hemodialysis clearance of Kyprolis concentrations has not been studied, the drug should be administered after the hemodialysis procedure.

Drug Interaction Studies

Clinical Studies

Effect of Carfilzomib on Sensitive CYP3A Substrate: Midazolam (a sensitive CYP3A substrate) pharmacokinetics was not affected by concomitant administration of carfilzomib.

In Vitro Studies

Effect of Carfilzomib on Cytochrome P450 (CYP) Enzymes: Carfilzomib showed direct and time-dependent inhibition of CYP3A but did not induce CYP1A2 and CYP3A4 in vitro.

Effect of Transporters on Carfilzomib: Carfilzomib is a P-glycoprotein (P-gp) substrate in vitro.

Effect of Carfilzomib on Transporters: Carfilzomib inhibits P-gp in vitro. However, given that Kyprolis is administered intravenously and is extensively metabolized, the pharmacokinetics of Kyprolis is unlikely to be affected by P-gp inhibitors or inducers.

13 NONCLINICAL TOXICOLOGY

13.1 Carcinogenesis, Mutagenesis, Impairment of Fertility

Carcinogenicity studies have not been conducted with carfilzomib.

Carfilzomib was clastogenic in the in vitro chromosomal aberration test in peripheral blood lymphocytes. Carfilzomib was not mutagenic in the in vitro bacterial reverse mutation (Ames) test and was not clastogenic in the in vivo mouse bone marrow micronucleus assay.

Fertility studies with carfilzomib have not been conducted. No effects on reproductive tissues were noted during 28-day repeat-dose rat and monkey toxicity studies or in 6-month rat and 9-month monkey chronic toxicity studies.

13.2 Animal Toxicology and/or Pharmacology

Cardiovascular Toxicity

Monkeys administered a single bolus intravenous dose of carfilzomib at 3 mg/kg (approximately 1.3 times recommended dose in humans of 27 mg/m^2 based on BSA) experienced hypotension, increased heart rate, and increased serum levels of troponin-T.

Chronic Administration

Repeated bolus intravenous administration of carfilzomib at ≥ 2 mg/kg/dose in rats and 2 mg/kg/dose in monkeys using dosing schedules similar to those used clinically resulted in mortalities that were due to toxicities occurring in the cardiovascular (cardiac failure, cardiac fibrosis, pericardial fluid accumulation, cardiac hemorrhage/degeneration), gastrointestinal (necrosis/hemorrhage), renal (glomerulonephropathy, tubular necrosis, dysfunction), and pulmonary (hemorrhage/inflammation) systems. The dose of 2 mg/kg/dose in rats is approximately half the recommended dose in humans of 27 mg/m^2 based on BSA. The dose of 2 mg/kg/dose in monkeys is approximately equivalent to the recommended dose in humans based on BSA.

14 CLINICAL STUDIES

14.1 In Combination with Lenalidomide and Dexamethasone for Relapsed or Refractory Multiple Myeloma

ASPIRE (NCT01080391)

ASPIRE was a randomized, open-label, multicenter trial which evaluated the combination of Kyprolis with lenalidomide and dexamethasone (KRd) versus lenalidomide and dexamethasone alone (Rd) in patients with relapsed or refractory multiple myeloma who had received 1 to 3 lines of therapy (A line of therapy is a planned course of treatment [including sequential induction, transplantation, consolidation, and/or maintenance] without an interruption for lack of efficacy, such as for relapse or progressive disease). Patients who had the following were excluded from the trial: refractory to bortezomib in the most recent regimen, refractory to lenalidomide and dexamethasone in the most recent regimen, not responding to any prior regimen, creatinine clearance < 50 mL/min, ALT/AST > 3.5 × ULN and bilirubin > 2 × ULN, New York Heart Association Class III to IV congestive heart failure, or myocardial infarction within the last 4 months.

In the KRd arm, Kyprolis was evaluated at a starting dose of 20 mg/m^2, which was increased to 27 mg/m^2 on Cycle 1, Day 8 onward. Kyprolis was administered as a 10-minute infusion on Days 1, 2, 8, 9, 15, and 16 of each 28-day cycle for Cycle 1 through 12. Kyprolis was dosed on Days 1, 2, 15, and 16 of each 28-day cycle from Cycle 13 through 18. Dexamethasone 40 mg was administered orally or intravenously on Days 1, 8, 15 and 22 of each cycle. Lenalidomide was given 25 mg orally on Days 1 to 21 of each 28-day cycle. The Rd treatment arm had the same regimen for lenalidomide and dexamethasone as the KRd treatment arm. Kyprolis was administered for a maximum of 18 cycles unless discontinued early for disease progression or unacceptable toxicity. Lenalidomide and dexamethasone administration could continue until progression or unacceptable toxicity. Concurrent use of thromboprophylaxis and a proton pump inhibitor were required for both arms and antiviral prophylaxis was required for the KRd arm.

The 792 patients in ASPIRE were randomized 1:1 to the KRd or Rd arm. The demographics and baseline characteristics were well-balanced between the two arms (see Table 22). Only 53% of the patients had testing for genetic mutations; a high-risk genetic mutation was identified for 12% of patients in the KRd arm and in 13% in the Rd arm.

Table 22: Demographics and Baseline Characteristics in ASPIRE
Characteristics | KRd (N = 396) | Rd (N = 396)
Age, Median, Years (min, max) | 64 (38, 87) | 65 (31, 91)
Age ≥ 75 Years, n (%) | 43 (11) | 53 (13)
Males, n (%) | 215 (54) | 232 (59)
Race, n (%)
White | 377 (95) | 377 (95)
Black | 12 (3) | 11 (3)
Other or Not Reported | 7 (2) | 8 (2)
Number of Prior Regimens, n (%)
1 | 184 (46) | 157 (40)
2 | 120 (30) | 139 (35)
3 [Including 2 patients with 4 prior regimens.] | 92 (23) | 100 (25)
Prior Transplantation, n (%) | 217 (55) | 229 (58)
ECOG Performance Status, n (%)
0 | 165 (42) | 175 (44)
1 | 191 (48) | 186 (47)
2 | 40 (10) | 35 (9)
ISS Stage at Study Baseline, n (%)
I | 167 (42) | 154 (39)
II | 148 (37) | 153 (39)
III | 73 (18) | 82 (21)
Unknown | 8 (2) | 7 (2)
Creatinine Clearance mL/min, Median (min, max) | 79 (39, 212) | 79 (30, 208)
30 to < 50, n (%) | 19 (5) | 32 (8)
50 to < 80, n (%) | 185 (47) | 170 (43)
Refractory to Last Therapy, n (%) | 110 (28) | 119 (30)
Refractory at Any Time to, n (%):
Bortezomib | 60 (15) | 58 (15)
Lenalidomide | 29 (7) | 28 (7)
Bortezomib + immunomodulatory agent | 24 (6) | 27 (7)
ECOG = Eastern Cooperative Oncology Group; IgG = immunoglobulin G; ISS = International Staging System; KRd = Kyprolis, lenalidomide, and dexamethasone; Rd = lenalidomide and dexamethasone

Patients in the KRd arm demonstrated improved PFS compared with those in the Rd arm (HR = 0.69, with 2-sided P-value = 0.0001) as determined using standard International Myeloma Working Group (IMWG)/European Blood and Marrow Transplantation (EBMT) response criteria by an Independent Review Committee (IRC). The median PFS was 26.3 months in the KRd arm versus 17.6 months in the Rd arm (see Table 23 and Figure 1).

A pre-planned overall survival (OS) analysis was performed after 246 deaths in the KRd arm and 267 deaths in the Rd arm. The median follow-up was approximately 67 months. A statistically significant advantage in OS was observed in patients in the KRd arm compared to patients in the Rd arm (see Table 23 and Figure 2).

Table 23: Efficacy Outcomes in ASPIRE [Eligible patients had 1-3 prior lines of therapy.]
 | Combination Therapy
 | KRd (N = 396) | Rd (N = 396)
PFS [As determined by an Independent Review Committee.]
Median [Based on Kaplan-Meier estimates.] , Months (95% CI) | 26.3 (23.3, 30.5) | 17.6 (15.0, 20.6)
HR (95% CI) [Based on stratified Cox's model.] | 0.69 (0.57, 0.83)
P-value (2-sided) [The P-value was derived using stratified log-rank test.] | 0.0001
Overall Survival
Median, Months (95% CI) | 48.3 (42.4, 52.8) | 40.4 (33.6, 44.4)
HR (95% CI) | 0.79 (0.67, 0.95)
P-value (2-sided) | 0.0091
Overall Response
N with response | 345 | 264
ORR (%) (95% CI) [Exact confidence interval.] | 87 (83, 90) | 67 (62, 71)
P-value (2-sided) [The P-value was derived using Cochran Mantel Haenszel test.] | < 0.0001
Response Category, n (%)
sCR | 56 (14) | 17 (4)
CR | 70 (18) | 20 (5)
VGPR | 151 (38) | 123 (31)
PR | 68 (17) | 104 (26)
CI = confidence interval; CR = complete response; HR = hazard ratio; KRd = Kyprolis, lenalidomide, and dexamethasone; ORR = overall response rate; PFS = progression-free survival; PR = partial response; Rd = lenalidomide and dexamethasone; sCR = stringent CR; VGPR = very good partial response

The median duration of response (DOR) was 28.6 months (95% CI: 24.9, 31.3) for the 345 patients achieving a response in the KRd arm and 21.2 months (95% CI: 16.7, 25.8) for the 264 patients achieving a response in the Rd arm. The median time to response was 1 month (range 1 to 14 months) in the KRd arm and 1 month (range 1 to 16 months) in the Rd arm.

Figure 1: Kaplan-Meier Curve of Progression-Free Survival in ASPIRE

CI = confidence interval; EBMT = European Blood and Marrow Transplantation; HR = hazard ratio; IMWG = International Myeloma Working Group; KRd = Kyprolis, lenalidomide, and dexamethasone; mo = months; PFS = progression-free survival; Rd = lenalidomide and dexamethasone arm
Note: The response and PD outcomes were determined using standard objective IMWG/EBMT response criteria.

Figure 2: Kaplan-Meier Curve of Overall Survival in ASPIRE

CI = confidence interval; HR = hazard ratio; KRd = Kyprolis, lenalidomide, and dexamethasone; mo = months; OS = overall survival; Rd = lenalidomide and dexamethasone arm

14.2 In Combination with Dexamethasone for Relapsed or Refractory Multiple Myeloma

The efficacy of Kyprolis in combination with dexamethasone was evaluated in two open-label randomized trials (ENDEAVOR and A.R.R.O.W.).

ENDEAVOR (NCT01568866)

ENDEAVOR was a randomized, open-label, multicenter trial of Kyprolis and dexamethasone (Kd) versus bortezomib and dexamethasone (Vd) in patients with relapsed or refractory multiple myeloma who had received 1 to 3 lines of therapy. A total of 929 patients were enrolled and randomized (464 in the Kd arm; 465 in the Vd arm). Randomization was stratified by prior proteasome inhibitor therapy (yes versus no), prior lines of therapy (1 versus 2 or 3), current International Staging System stage (1 versus 2 or 3), and planned route of bortezomib administration. Patients were excluded if they had less than PR to all prior regimens; creatinine clearance < 15 mL/min; hepatic transaminases ≥ 3 × ULN; or left-ventricular ejection fraction < 40% or other significant cardiac conditions.

This trial evaluated Kyprolis at a starting dose of 20 mg/m^2, which was increased to 56 mg/m^2 on Cycle 1, Day 8 onward. Kyprolis was administered twice weekly as a 30-minute infusion on Days 1, 2, 8, 9, 15, and 16 of each 28-day cycle. Dexamethasone 20 mg was administered orally or intravenously on Days 1, 2, 8, 9, 15, 16, 22, and 23 of each cycle. In the Vd arm, bortezomib was dosed at 1.3 mg/m^2 intravenously or subcutaneously on Days 1, 4, 8, and 11 of a 21-day cycle, and dexamethasone 20 mg was administered orally or intravenously on Days 1, 2, 4, 5, 8, 9, 11, and 12 of each cycle. Concurrent use of thromboprophylaxis was optional, and prophylaxis with an antiviral agent and proton pump inhibitor was required. Of the 465 patients in the Vd arm, 381 received bortezomib subcutaneously. Treatment continued until disease progression or unacceptable toxicity.

The demographics and baseline characteristics are summarized in Table 24.

Table 24: Demographics and Baseline Characteristics in ENDEAVOR
Characteristics | Kd (N = 464) | Vd (N = 465)
Age, Years
Median (min, max) | 65 (35, 89) | 65 (30, 88)
< 65, n (%) | 223 (48) | 210 (45)
65 – 74, n (%) | 164 (35) | 189 (41)
≥ 75, n (%) | 77 (17) | 66 (14)
Sex, n (%)
Female | 224 (48) | 236 (51)
Male | 240 (52) | 229 (49)
Race, n (%)
White | 353 (76) | 361 (78)
Black | 7 (2) | 9 (2)
Asian | 56 (12) | 57 (12)
Other or Not Reported | 48 (10) | 38 (8)
ECOG Performance Status, n (%)
0 | 221 (48) | 232 (50)
1 | 210 (45) | 203 (44)
2 | 33 (7) | 30 (6)
Creatinine Clearance (mL/min)
Median (min, max) | 73 (14, 185) | 72 (12, 208)
< 30, n (%) | 28 (6) | 28 (6)
30 – < 50, n (%) | 57 (12) | 71 (15)
50 – < 80, n (%) | 186 (40) | 177 (38)
≥ 80, n (%) | 193 (42) | 189 (41)
FISH, n (%)
High-risk | 97 (21) | 113 (24)
Standard-risk | 284 (61) | 291 (63)
Unknown-risk | 83 (18) | 61 (13)
ISS Stage at Study Baseline, n (%)
ISS I | 219 (47) | 212 (46)
ISS II | 138 (30) | 153 (33)
ISS III | 107 (23) | 100 (22)
Number of Prior Regimens, n (%)
1 | 232 (50) | 231 (50)
2 | 158 (34) | 144 (31)
3 | 74 (16) | 88 (19)
4 | 0 (0) | 2 (0.4)
Prior Therapies, n (%) | 464 (100) | 465 (100)
Bortezomib | 250 (54) | 252 (54)
Transplant for Multiple Myeloma | 266 (57) | 272 (59)
Thalidomide | 212 (46) | 249 (54)
Lenalidomide | 177 (38) | 178 (38)
Bortezomib + immunomodulatory agent | 159 (34) | 168 (36)
Refractory to last prior therapy, n (%) [Refractory = disease not achieving a minimal response or better, progressing during therapy, or progressing within 60 days after completion of therapy.] | 184 (40) | 189 (41)
ECOG = Eastern Cooperative Oncology Group; FISH = Fluorescence in situ hybridization; ISS = International Staging System; Kd = Kyprolis and dexamethasone; Vd = bortezomib and dexamethasone

The efficacy of Kyprolis was evaluated by PFS as determined by an IRC using IMWG response criteria. The trial showed a median PFS of 18.7 months in the Kd arm versus 9.4 months in the Vd arm (see Table 25 and Figure 3).

Figure 3: Kaplan-Meier Plot of Progression-Free Survival in ENDEAVOR

CI = confidence interval; HR = hazard ratio; Kd = Kyprolis and dexamethasone; mo = months; PFS = progression-free survival; Vd = bortezomib and dexamethasone

Other endpoints included OS and overall response rate (ORR).

A pre-planned OS analysis was performed after 189 deaths in the Kd arm and 209 deaths in the Vd arm. The median follow-up was approximately 37 months. A significantly longer OS was observed in patients in the Kd arm compared to patients in the Vd arm (HR = 0.79; 95% CI: 0.65, 0.96; P-value = 0.01). Results are provided in Table 25 and Figure 4.

Table 25: Summary of Key Results in ENDEAVOR (Intent-to-Treat Population) [Eligible patients had 1-3 prior lines of therapy.]
 | Kd (N = 464) | Vd (N = 465)
PFS [PFS and ORR were determined by an Independent Review Committee.]
Number of events (%) | 171 (37) | 243 (52)
Median [Based on Kaplan-Meier estimates.] , Months (95% CI) | 18.7 (15.6, NE) | 9.4 (8.4, 10.4)
HR (Kd/Vd) (95% CI) [Based on a stratified Cox's model.] | 0.53 (0.44, 0.65)
P-value (1-sided) [P-value was derived using a stratified log-rank test.] | < 0.0001
Overall Survival
Number of deaths (%) | 189 (41) | 209 (45)
Median, Months (95% CI) | 47.6 (42.5, NE) | 40.0 (32.6, 42.3)
HR (Kd/Vd) (95% CI) | 0.79 (0.65, 0.96)
P-value (1-sided) | 0.01
Overall Response
N with Response | 357 | 291
ORR (%) (95% CI) [Exact confidence interval.] | 77 (73, 81) | 63 (58, 67)
P-value (1-sided) [The P-value was derived using Cochran Mantel Haenszel test.] | < 0.0001
Response Category, n (%)
sCR | 8 (2) | 9 (2)
CR | 50 (11) | 20 (4)
VGPR | 194 (42) | 104 (22)
PR [Includes one patient in each arm with a confirmed PR which may not have been the best response.] | 105 (23) | 158 (34)
CI = confidence interval; CR = complete response; HR= hazard ratio; Kd = Kyprolis and dexamethasone; ORR = overall response rate; PFS = progression-free survival; PR = partial response; sCR = stringent CR; Vd = bortezomib and dexamethasone; VGPR = very good partial response; NE = non-estimable

Figure 4: Kaplan-Meier Plot of Overall Survival in ENDEAVOR

CI = confidence interval; HR = hazard ratio; Kd = Kyprolis and dexamethasone; mo = month; OS = overall survival; Vd = bortezomib and dexamethasone

The median DOR in subjects achieving PR or better was 21.3 months (95% CI: 21.3, not estimable) in the Kd arm and 10.4 months (95% CI: 9.3, 13.8) in the Vd arm. The median time to response was 1 month (range < 1 to 8 months) in both arms.

A.R.R.O.W. (NCT02412878)

A.R.R.O.W. was a randomized, open-label, multicenter superiority trial of Kyprolis and dexamethasone (Kd) once weekly (20/70 mg/m^2) versus Kd twice weekly (20/27 mg/m^2) in patients with relapsed and refractory multiple myeloma who had received 2 to 3 prior lines of therapy. Patients were excluded if they had less than PR to at least one prior line; creatinine clearance < 30 mL/min; hepatic transaminases ≥ 3 × ULN; or left-ventricular ejection fraction < 40% or other significant cardiac conditions. A total of 478 patients were enrolled and randomized (240 in 20/70 mg/m^2 arm; 238 in 20/27 mg/m^2 arm). Randomization was stratified by current International Staging System stage (stage 1 versus stages 2 or 3), refractory to bortezomib treatment (yes versus no), and age (< 65 versus ≥ 65 years).

Arm 1 of this trial evaluated Kyprolis at a starting dose of 20 mg/m^2, which was increased to 70 mg/m^2 on Cycle 1, Day 8 onward. Arm 1 Kyprolis was administered once weekly as a 30-minute infusion on Days 1, 8 and 15, of each 28-day cycle. Arm 2 of this trial evaluated Kyprolis at a starting dose of 20 mg/m^2, which was increased to 27 mg/m^2 on Cycle 1, Day 8 onward. Arm 2 Kyprolis was administered twice weekly as a 10-minute infusion on Days 1, 2, 8, 9, 15, and 16 of each 28-day cycle. In both regimens, dexamethasone 40 mg was administered orally or intravenously on Days 1, 8, 15 for all cycles and on Day 22 for cycles 1 to 9 only. Concurrent use of thromboprophylaxis was optional, prophylaxis with an antiviral agent was recommended, and prophylaxis with a proton pump inhibitor was required. Treatment continued until disease progression or unacceptable toxicity.

The demographics and baseline characteristics are summarized in Table 26.

Table 26: Demographics and Baseline Characteristics in A.R.R.O.W.
Characteristics | Once weekly Kd 20/70 mg/m^2 (N = 240) | Twice weekly Kd 20/27 mg/m^2 (N = 238)
Age, Years
Median (min, max) | 66 (39, 85) | 66 (35, 83)
< 65, n (%) | 104 (43) | 104 (44)
65 – 74, n (%) | 90 (38) | 102 (43)
≥ 75, n (%) | 46 (19) | 32 (13)
Sex, n (%)
Female | 108 (45) | 110 (46)
Male | 132 (55) | 128 (54)
Race, n (%)
White | 200 (83) | 202 (85)
Black | 3 (1) | 2 (1)
Asian | 30 (13) | 15 (6)
Other or Not Reported | 7 (3) | 19 (8)
ECOG Performance Status, n (%)
0 | 118 (49) | 118 (50)
1 | 121 (50) | 120 (50)
2 | 1 (0.4) | 0 (0)
Creatinine Clearance (mL/min)
Median (min, max) | 70.80 (28, 212) | 73.20 (29, 181)
< 30, n (%) | 2 (1) | 1 (0.4)
30 – < 50, n (%) | 48 (20) | 34 (14)
50 – < 80, n (%) | 91 (38) | 111 (47)
≥ 80, n (%) | 99 (41) | 91 (38)
FISH, n (%)
High-risk | 34 (14) | 47 (20)
Standard-risk | 47 (20) | 53 (22)
Unknown-risk | 159 (66) | 138 (58)
ISS Stage at Study Baseline, n (%)
ISS I | 94 (39) | 99 (42)
ISS II | 80 (33) | 81 (34)
ISS III | 63 (26) | 54 (23)
Number of Prior Regimens, n (%)
2 | 116 (48) | 125 (53)
3 | 124 (52) | 112 (47)
>3 | 0 (0) | 1 (0.4)
Prior Therapies, n (%)
Bortezomib | 236 (98) | 237 (100)
Transplantation | 146 (61) | 157 (66)
Thalidomide | 119 (50) | 119 (50)
Lenalidomide | 207 (86) | 194 (82)
ECOG = Eastern Cooperative Oncology Group; FISH = Fluorescence in situ hybridization; ISS = International Staging System; Kd = Kyprolis and dexamethasone

The efficacy of Kyprolis was evaluated by PFS using IMWG response criteria. Efficacy results are provided in Table 27 and Figure 5.

Figure 5: Kaplan-Meier Plot of Progression-Free Survival in A.R.R.O.W.

CI = confidence interval; HR = hazard ratio; Kd = Kyprolis and dexamethasone; PFS = progression-free survival

Table 27: Summary of Key Results in A.R.R.O.W. (Intent-to-Treat Population)
 | Once weekly Kd 20/70 mg/m^2 (N = 240) | Twice weekly Kd 20/27 mg/m^2 (N = 238)
PFS
Number of events, n (%) | 126 (52.5) | 148 (62.2)
Median, Months (95% CI) | 11.2 (8.6, 13.0) | 7.6 (5.8, 9.2)
HR (95% CI) | 0.69 (0.54, 0.88)
P-value (1-sided) | 0.0014
Overall Response [Overall response is defined as achieving a best overall response of PR, VGPR, CR or sCR.]
N with Response | 151 | 97
ORR (%) (95% CI) | 62.9 (56.5, 69.0) | 40.8 (34.5, 47.3)
P-value (1-sided) | < 0.0001
Response Category, n (%)
sCR | 4 (1.7) | 0 (0.0)
CR | 13 (5.4) | 4 (1.7)
VGPR | 65 (27.1) | 28 (11.8)
PR | 69 (28.8) | 65 (27.3)
CI = confidence interval; CR = complete response; HR = hazard ratio; Kd = Kyprolis and dexamethasone; ORR = overall response rate; PFS = progression-free survival; PR = partial response; sCR = stringent complete response; VGPR = very good partial response

The median DOR in subjects achieving PR or better was 15 months (95% CI: 12.2, not estimable) in the Kd 20/70 mg/m^2 arm and 13.8 months (95% CI: 9.5, not estimable) in the Kd 20/27 mg/m^2 arm. The median time to response was 1.1 months in the Kd 20/70 mg/m^2 arm and 1.9 months in the Kd 20/27 mg/m^2 arm.

Kyprolis is not approved for twice weekly 20/27 mg/m^2 administration in combination with dexamethasone alone.

14.3 In Combination with Daratumumab and Dexamethasone for Relapsed or Refractory Multiple Myeloma

The efficacy of Kyprolis in combination with daratumumab and dexamethasone or daratumumab and hyaluronidase-fihj and dexamethasone (DKd) was evaluated in three open-label clinical trials (CANDOR, EQUULEUS, and PLEIADES).

CANDOR (NCT03158688)

CANDOR was a randomized, open-label, multicenter trial which evaluated the combination of Kyprolis 20/56 mg/m^2 twice weekly with intravenous daratumumab and dexamethasone (DKd) versus Kyprolis 20/56 mg/m^2 twice weekly and dexamethasone (Kd) in patients with relapsed or refractory multiple myeloma who had received 1 to 3 prior lines of therapy. Patients who had the following were excluded from the trial: known moderate or severe persistent asthma within the past 2 years, known chronic obstructive pulmonary disease (COPD) with a FEV1 < 50% of predicted normal, and active congestive heart failure. Randomization was stratified by the ISS (stage 1 or 2 vs stage 3) at screening, prior proteasome inhibitor exposure (yes vs no), number of prior lines of therapy (1 vs ≥ 2), or prior cluster differentiation antigen 38 (CD38) antibody therapy (yes vs no).

Kyprolis was administered intravenously over 30 minutes at a dose of 20 mg/m^2 in Cycle 1 on Days 1 and 2; at a dose of 56 mg/m^2 in Cycle 1 on Days 8, 9, 15 and 16; and on Days 1, 2, 8, 9, 15 and 16 of each 28-day cycle thereafter. Dexamethasone 20 mg was administered orally or intravenously on Days 1, 2, 8, 9, 15 and 16 and then 40 mg orally or intravenously on Day 22 of each 28-day cycle. In the DKd arm, daratumumab was administered intravenously at a dose of 8 mg/kg in Cycle 1 on Days 1 and 2. Thereafter, daratumumab was administered intravenously at a dose of 16 mg/kg on Days 8, 15 and 22 of Cycle 1; Days 1, 8 and 15 and 22 of Cycle 2; Days 1 and 15 of Cycles 3 to 6; and Day 1 for the remaining cycles or until disease progression. For patients >75 years on a reduced dexamethasone dose of 20 mg, the entire 20 mg dose was given as a daratumumab pre-infusion medication on days when daratumumab was administered. Dosing of dexamethasone was otherwise split across days when Kyprolis was administered in both study arms. Treatment was continued in both arms until disease progression or unacceptable toxicity.

A total of 466 patients were randomized; 312 to the DKd arm and 154 to the Kd arm. The demographics and baseline characteristics are summarized in Table 28.

Table 28: Demographics and Baseline Characteristics in CANDOR
Characteristics | DKd (N = 312) | Kd (N = 154)
Age at randomization (years)
Median (min, max) | 64 (29, 84) | 65 (35, 83)
Age group – n (%)
18 – 64 years | 163 (52) | 77 (50)
65 – 74 years | 121 (39) | 55 (36)
75 years and older | 28 (9) | 22 (14)
Sex – n (%)
Male | 177 (57) | 91 (59)
Female | 135 (43) | 63 (41)
Race – n (%)
Asian | 46 (15) | 20 (13)
Black or African American | 7 (2.2) | 2 (1.3)
White | 243 (78) | 123 (80)
Other | 16 (5) | 9 (6)
Geographic region – n (%)
North America | 21 (7) | 12 (8)
Europe | 207 (66) | 103 (67)
Asia Pacific | 84 (27) | 39 (25)
ECOG performance status – n (%)
0 or 1 | 295 (95) | 147 (95)
2 | 15 (4.8) | 7 (4.5)
Missing | 2 (0.6) | 0 (0.0)
Risk group as determined by FISH – n (%)
High risk | 48 (15) | 26 (17)
Standard risk | 104 (33) | 52 (34)
Unknown | 160 (51) | 76 (49)
ISS stage per I × RS at screening – n (%)
I or II | 252 (81) | 127 (82)
III | 60 (19) | 27 (17)
Number of prior regimens – n (%) [Subjects with number of prior regimens > 3 was 0 in the DKd arm and 1 in Kd arm.]
1 | 144 (46) | 70 (45)
2 | 99 (32) | 46 (30)
3 | 69 (22) | 37 (24)
Prior Therapies
Lenalidomide | 123 (39) | 74 (48)
Refractory to lenalidomide | 99 (32) | 55 (36)
Bortezomib | 287 (92) | 134 (87)
Prior CD38 antibody therapy – n (%) | 1 (0.3) | 0 (0.0)
Prior stem cell transplant (ASCT) – n (%) | 195 (62) | 75 (49)
DKd = Kyprolis, daratumumab, and dexamethasone; ECOG = Eastern Cooperative Oncology Group; FISH = Fluorescence in situ hybridization; ISS = International Staging System; Kd = Kyprolis and dexamethasone

Efficacy was assessed by an IRC evaluation of PFS using the IMWG response criteria. Efficacy results are provided in Table 29 and Figure 6. The median duration of response has not been reached for the DKd arm and was 16.6 months (13.9, NE) for the Kd arm. The median (min, max) time to response was 1.0 (1, 14) months for the DKd arm and 1.0 (1, 10) months for the Kd arm.

Figure 6: Kaplan-Meier Plot of Progression-Free Survival in CANDOR

CI = confidence interval; DKd = Kyprolis, daratumumab and dexamethasone; HR = hazard ratio; Kd= Kyprolis and dexamethasone

Table 29: Summary of Key Results in CANDOR (IntenttoTreat Population)
 | DKd (N = 312) | Kd (N = 154)
PFS
Number of events (%) | 110 (35%) | 68 (44%)
Median, Months (95% CI) | NE (NE, NE) | 15.8 (12.1, NE)
HR (95% CI) | 0.63 (0.46, 0.85)
P-value (1-sided) [The P-value was derived using stratified log-rank test] | 0.0014
Overall Response
N with Response | 263 | 115
ORR (%) (95% CI) | 84% (80%, 88%) | 75% (67%, 81%)
P-value (1-sided) [The P-value was derived using stratified Cochran Mantel-Haenszel Chi-Squared test] | 0.0040
CR | 89 (28%) | 16 (10%)
VGPR | 127 (41%) | 59 (38%)
PR | 47 (15%) | 40 (26%)
MRD [-] CR rate at 12 months n (%) [MRD [-] CR (at a 10^-5 level) is defined as achievement of CR per IMWG-URC and MRD[-] status as assessed by the next-generation sequencing assay (ClonoSEQ) at the 12 months landmark (from 8 months to 13 months window)] | 39 (12%) | 2 (1.3%)
(95% CI) | (9%, 17%) | (0.2%, 4.6%)
P-value (1-sided) | < 0.0001
MRD [-] CR [MRD[-]CR (at a 10^-5 level) is defined as achievement of CR per IMWG-URC and MRD[-] status as assessed by the next-generation sequencing assay (ClonoSEQ) at any timepoint during the trial] | 43 (14%) | 5 (3.2%)
CI = confidence interval; CR = complete response; HR = hazard ratio; DKd = Kyprolis, daratumumab, and dexamethasone; Kd = Kyprolis and dexamethasone; ORR = overall response rate; PFS = progression-free survival; PR = partial response; MRD [-] CR = minimal residual disease negative-complete response; NE = non-estimable; VGPR = very good partial response

EQUULEUS (NCT01998971)

EQUULEUS was an open-label, multi-cohort trial which evaluated the combination of Kyprolis with intravenous daratumumab and dexamethasone in patients with relapsed or refractory multiple myeloma who had received 1 to 3 prior lines of therapy. Patients who had the following were excluded from the trial: known moderate or severe persistent asthma within the past 2 years, known chronic obstructive pulmonary disease (COPD) with a FEV1 < 50% of predicted normal, or active congestive heart failure (defined as New York Heart Association Class III-IV).

Kyprolis was administered intravenously over 30 minutes once weekly at a dose of 20 mg/m^2 on Cycle 1 Day 1 and escalated to a dose of 70 mg/m^2 on Cycle 1, Days 8 and 15; and on Days 1, 8, and 15 of each 28-day cycle. Ten patients were administered daratumumab at a dose of 16 mg/kg intravenously on Cycle 1, Day 1 and the remaining patients were administered daratumumab at a dose of 8 mg/kg intravenously on Cycle 1, Days 1 and 2. Thereafter, daratumumab was administered intravenously at a dose of 16 mg/kg on Days 8, 15 and 22 of Cycle 1; Days 1, 8, 15 and 22 of Cycle 2; Days 1 and 15 of Cycles 3 to 6; and then Day 1 for the remaining cycles of each 28-day cycle. In Cycles 1 and 2, dexamethasone 20 mg was administered orally or intravenously on Days 1, 2, 8, 9, 15, 16, 22 and 23; in cycles 3 to 6, dexamethasone 20 mg was administered orally or intravenously on Days 1, 2, 15 and 16 and at a dose of 40 mg on Day 8 and 22; and in cycles 7 and thereafter, dexamethasone 20 mg was administered orally or intravenously on Days 1 and 2 and at a dose of 40 mg on Days 8, 15, and 22. For patients > 75 years of age, dexamethasone 20 mg was administered orally or intravenously weekly after the first week. Treatment continued until disease progression or unacceptable toxicity.

The EQUULEUS trial enrolled 85 patients. The demographics and baseline characteristics are summarized in Table 30.

Table 30: Demographics and Baseline Characteristics in DKd 20/70 mg/m^2 Regimen of EQUULEUS (Combination Therapy for Relapsed or Refractory Multiple Myeloma)
Characteristics | Number of Patients (%)
Age (years)
Median (min, max) | 66 (38, 85)
Age group – n (%)
< 65 years | 36 (42)
65 - < 75 years | 41 (48)
≥ 75 years | 8 (9)
Sex – n (%)
Male | 46 (54)
Female | 39 (46)
Race – n (%)
Asian | 3 (3.5)
Black or African American | 3 (3.5)
White | 68 (80)
ECOG Score, n (%)
0 | 32 (38)
1 | 46 (54)
2 | 7 (8)
FISH, n (%)
N | 67
Standard Risk | 54 (81)
High Risk | 13 (19)
Number of Prior regimens
1 | 20 (23)
2 | 40 (47)
3 | 23 (27)
> 3 | 2 (2.4)
Prior Therapies
Bortezomib | 85 (100)
Lenalidomide | 81 (95)
Prior stem cell transplant (ASCT) | 62 (73)
Refractory to lenalidomide | 51 (60)
Refractory to both a PI and IMiD | 25 (29)
ECOG = Eastern Cooperative Oncology Group; FISH = Fluorescence in situ hybridization; PI = proteasome inhibitor; IMiD = immunomodulatory agent.

Efficacy results were based on overall response rate using IMWG criteria. Efficacy results are provided in Table 31. The median time to response was 0.95 months (range: 0.9, 14.3). The median duration of response was 28 months (95% CI: 20.5, not estimable).

Table 31: Summary of Key Results in EQUULEUS (IntenttoTreat Population)
 | Study Patients n (%)
Overall Response
N with Response | 69
ORR (%) (95% CI) | 81% (71, 89)
Response category, n (%)
sCR | 18 (21%)
CR | 12 (14%)
VGPR | 28 (33%)
PR | 11 (13%)
CI = confidence interval; sCR = stringent complete response; CR = complete response; ORR = overall response rate; PR = partial response; VGPR = very good partial response

PLEIADES (NCT03412565)

The efficacy of Kyprolis with daratumumab and hyaluronidase-fihj plus dexamethasone (DKd) was evaluated in a single-arm cohort of PLEIADES, a multi-cohort, open-label trial. This cohort enrolled patients with relapsed or refractory multiple myeloma excluding patients with left ventricular ejection fraction (LVEF) less than 40%, myocardial infarction within 6 months, uncontrolled cardiac arrhythmia, or uncontrolled hypertension (systolic blood pressure >159 mmHg or diastolic >99 mmHg despite optimal treatment). Patients received Kyprolis administered by IV infusion at a dose of 20 mg/m^2 on Cycle 1 Day 1 and if a dose of 20 mg/m^2 was tolerated Kyprolis was administered at a dose of 70 mg/m^2 as a 30-minute IV infusion on Cycle 1 Day 8 and Day 15, and then Day 1, 8 and 15 of each cycle; daratumumab and hyaluronidase-fihj1,800 mg/30,000 units administered subcutaneously once weekly from Weeks 1 to 8, once every 2 weeks from Weeks 9 to 24 and once every 4 weeks starting with Week 25 until disease progression or unacceptable toxicity; and dexamethasone 40 mg per week (or a reduced dose of 20 mg per week for patients ≥75 years or BMI <18.5). The major efficacy outcome measure was ORR.

A total of 66 patients received the DKd regimen. The median age was 61 years (range: 42, 84); 52% were male; 73% were White and 3% Black or African American; and 68% had ISS Stage I, 18% had ISS Stage II, and 14% had ISS Stage III disease. A total of 79% of patients had a prior ASCT; 91% of patients received a prior PI. All patients received 1 prior line of therapy with exposure to lenalidomide and 62% of patients were refractory to lenalidomide.

Efficacy results are summarized in Table 32. At a median follow-up of 9.2 months, the median duration of response had not been reached and an estimated 85.2% (95% CI: 72.5, 92.3) maintained response for at least 6 months and 82.5% (95% CI: 68.9, 90.6) maintained response for at least 9 months.

Table 32: Efficacy Results from PLEIADES in Patients Who Received DKd
 | DKd (N=66)
Overall response rate (sCR+CR+VGPR+PR), n (%) [Based on treated patients] | 56 (84.8%)
95% CI (%) | (73.9%, 92.5%)
Stringent complete response (sCR) | 11 (16.7%)
Complete response (CR) | 14 (21.2%)
Very good partial response (VGPR) | 26 (39.4%)
Partial response (PR) | 5 (7.6%)
CI = confidence interval

14.4 In Combination with Isatuximab and Dexamethasone for Relapsed or Refractory Multiple Myeloma

IKEMA (NCT03275285)

The efficacy and safety of Kyprolis in combination with isatuximab and dexamethasone were evaluated in IKEMA, a multicenter, multinational, randomized, open-label, 2-arm, phase 3 study in patients with relapsed and/or refractory multiple myeloma. Patients had received one to three prior lines of therapy. Patients were eligible for inclusion if they had an ECOG status of 0-2, platelets ≥50,000 cells/mm^3, absolute neutrophil count ≥1 × 10^9/L, creatinine clearance ≥15 mL/min/1.73 m^2 (MDRD formula), AST ≤3 × ULN, and ALT ≤3 × ULN.

A total of 302 patients were randomized in a 3:2 ratio to receive either Kyprolis in combination with isatuximab and dexamethasone (Isa-Kd, 179 patients) or Kyprolis and dexamethasone (Kd, 123 patients). Treatment was administered in both groups in 28-day cycles until disease progression or unacceptable toxicity. Isatuximab 10 mg/kg was administered as an intravenous infusion weekly in the first cycle and every two weeks thereafter. Kyprolis was administered as an intravenous infusion at the dose of 20 mg/m^2 on days 1 and 2; 56 mg/m^2 on days 8, 9, 15, and 16 of cycle 1; and at the dose of 56 mg/m^2 on days 1, 2, 8, 9, 15, and 16 for subsequent cycles of each 28-day cycle. Dexamethasone (intravenously on the days of isatuximab and/or Kyprolis infusions, and orally on the other days) 20 mg was given on days 1, 2, 8, 9, 15, 16, 22, and 23 for each 28-day cycle. On the days where both Kyprolis and isatuximab were administered, dexamethasone was administered first, followed by isatuximab infusion, then followed by Kyprolis infusion.

Overall, demographic and disease characteristics at baseline were similar between the two treatment groups. The median patient age was 64 years (range 33-90), 9% of patients were ≥ 75 years, 71% were White, 17% Asian, and 3% Black or African American. The proportion of patients with renal impairment (eGFR < 60 mL/min/1.73 m^2) was 24% in the Isa-Kd group versus 15% in the Kd group. The International Staging System (ISS) stage at study entry was I in 53%, II in 31%, and III in 15% of patients. Overall, 24% of patients had high-risk chromosomal abnormalities at study entry; del(17p), t(4;14), t(14;16) were present in 11%, 14%, and 2% of patients, respectively. In addition, gain(1q21) was present in 42% of patients.

The median number of prior lines of therapy was 2 (range 1-4) with 44% of patients who received 1 prior line of therapy. Overall, 90% of patients received prior proteasome inhibitors, 78% received prior immunomodulators (including 43% who received prior lenalidomide), and 61% received prior stem cell transplantation. Overall, 33% of patients were refractory to prior proteasome inhibitors, 45% were refractory to prior immunomodulators (including 33% refractory to lenalidomide), and 21% were refractory to both a proteasome inhibitor and an immunomodulator.

The median duration of treatment was 80 weeks for the Isa-Kd group compared to 61 weeks for the Kd group.

Efficacy was based upon PFS. PFS results were assessed by an Independent Response Committee based on central laboratory data for M-protein and central radiologic imaging review using the IMWG criteria. The improvement in PFS represented a 45% reduction in the risk of disease progression or death in patients treated with Isa-Kd compared to patients treated with Kd.

Efficacy results are presented in Table 33.

Table 33 [Results are based on a prespecified interim analysis.] [Median follow-up time 20.7 months.] : Efficacy of Kyprolis in Combination with Isatuximab and Dexamethasone versus Kyprolis and Dexamethasone in the Treatment of Multiple Myeloma (IKEMA)
Endpoint | Isa-Kd N=179 | Kd N=123
Progression-Free Survival [PFS results were assessed by the IRC based on central laboratory data for M-protein and central radiologic imaging review using the IMWG criteria. A comparison is considered statistically significant if the p-value is <0.008 (efficacy boundary).]
Median (months) [95% CI] | NR [NR- NR] | 20.27 [15.77- NR]
Hazard ratio [Stratified on number of previous lines of therapy (1 versus >1) and R-ISS (I or II versus III versus not classified) according to IRT.] [95% CI] | 0.548 [0.366-0.822]
p-value (stratified log-rank test) | 0.0032
Overall Response Rate [sCR, CR, VGPR, and PR were evaluated by the IRC using the IMWG response criteria.] Responders (sCR+CR+VGPR+PR) n (%) [95% CI] [Estimated using Clopper-Pearson method.] | 155 (86.6) [80.7-91.2] | 102 (82.9) [75.1-89.1]
p-value (stratified Cochran-Mantel-Haenszel) | 0.3859
Complete Response (CR) n (%) | 71 (39.7) | 34 (27.6)
Very Good Partial Response (VGPR) n (%) | 59 (33) | 35 (28.5)
Partial Response (PR) n (%) | 25 (14) | 33 (26.8)
NR: not reached.

Figure 7: Kaplan-Meier Plot of Progression-Free Survival in IKEMA

14.5 Monotherapy for Relapsed or Refractory Multiple Myeloma

Study PX-171-007 (NCT00531284)

Study PX-171-007 was a multicenter, open-label, dose escalation, single-arm trial that evaluated the safety of Kyprolis monotherapy as a 30-minute infusion in patients with relapsed or refractory multiple myeloma after 2 or more lines of therapy. Patients were excluded if they had a creatinine clearance < 20 mL/min; ALT ≥ 3 × upper limit of normal (ULN), bilirubin ≥ 1.5 × ULN; New York Heart Association Class III or IV congestive heart failure; or other significant cardiac conditions. A total of 24 subjects with multiple myeloma were enrolled at the maximum tolerated dose level of 20/56 mg/m^2. Kyprolis was administered twice weekly for 3 consecutive weeks (Days 1, 2, 8, 9, 15, and 16) of a 28-day cycle. In Cycle 13 onward, the Day 8 and 9 Kyprolis doses could be omitted. Patients received Kyprolis at a starting dose of 20 mg/m^2 on Days 1 and 2 of Cycle 1, which was increased to 56 mg/m^2 for all subsequent doses. Dexamethasone 8 mg orally or intravenously was required prior to each Kyprolis dose in Cycle 1 and was optional in subsequent cycles. Treatment was continued until disease progression or unacceptable toxicity.

Efficacy was evaluated by ORR and DOR. ORR by investigator assessment was 50% (95% CI: 29, 71) per IMWG criteria (see Table 34). The median DOR in subjects who achieved a PR or better was 8.0 months (Range: 1.4, 32.5).

Table 34: Response Categories in Study PX-171-007 (20/56 mg/m^2 Monotherapy Regimen)
Characteristics | Study Patients [Eligible patients had 2 or more prior lines of therapy.] n (%)
Number of Patients (%) | 24 (100)
Overall Response [Per investigator assessment.] | 12 (50)
95% CI [Exact confidence interval.] | (29, 71)
Response Category
sCR | 1 (4)
CR | 0 (0)
VGPR | 4 (17)
PR | 7 (29)
CI = confidence interval; CR = complete response; PR = partial response; sCR = stringent complete response; VGPR = very good partial response

Study PX-171-003 A1 (NCT00511238)

Study PX-171-003 A1 was a single-arm, multicenter clinical trial of Kyprolis monotherapy by up to 10-minute infusion. Eligible patients were those with relapsed and refractory multiple myeloma who had received at least two prior therapies (including bortezomib and thalidomide and/or lenalidomide) and had ≤ 25% response to the most recent therapy or had disease progression during or within 60 days of the most recent therapy. Patients were excluded from the trial if they were refractory to all prior therapies or had a total bilirubin ≥ 2 × ULN; creatinine clearance < 30 mL/min; New York Heart Association Class III to IV congestive heart failure; symptomatic cardiac ischemia; myocardial infarction within the last 6 months; peripheral neuropathy Grade 3 or 4, or peripheral neuropathy Grade 2 with pain; active infections requiring treatment; or pleural effusion.

Kyprolis was administered intravenously up to 10 minutes on two consecutive days each week for three weeks, followed by a 12-day rest period (28-day treatment cycle), until disease progression, unacceptable toxicity, or for a maximum of 12 cycles. Patients received 20 mg/m^2 at each dose in Cycle 1, and 27 mg/m^2 in subsequent cycles. Dexamethasone 4 mg orally or intravenously was administered prior to Kyprolis doses in the first and second cycles.

A total of 266 patients were enrolled. Baseline patient and disease characteristics are summarized in Table 35.

Table 35: Demographics and Baseline Characteristics in Study PX-171-003 A1 (20/27 mg/m^2 Monotherapy Regimen)
Characteristics | Number of Patients (%)
Patient Characteristics
Enrolled patients | 266 (100)
Median age, years (range) | 63 (37, 87)
Age group, < 65 / ≥ 65 (years) | 146 (55) / 120 (45)
Sex (male / female) | 155 (58) / 111 (42)
Race (White / Black / Asian / Other) | 190 (71) / 53 (20) / 6 (2) / 17 (6)
Disease Characteristics
Number of Prior Regimens (median) | 5 [Range: 1, 20.]
Prior Transplantation | 198 (74)
Refractory Status to Most Recent Therapy [Categories for refractory status are derived by programmatic assessment using available laboratory data.]
Refractory: Progression during most recent therapy | 198 (74)
Refractory: Progression within 60 days after completion of most recent therapy | 38 (14)
Refractory: ≤ 25% response to treatment | 16 (6)
Relapsed: Progression after 60 days post treatment | 14 (5)
Years since diagnosis, median (range) | 5.4 (0.5, 22.3)
Plasma cell involvement (< 50% / ≥ 50% / unknown) | 143 (54) / 106 (40) / 17 (6)
ISS Stage at Study Baseline
I | 76 (29)
II | 102 (38)
III | 81 (31)
Unknown | 7 (3)
Cytogenetics or FISH analyses
Normal/Favorable | 159 (60)
Poor Prognosis | 75 (28)
Unknown | 32 (12)
Creatinine clearance < 30 mL/min | 6 (2)
FISH = Fluorescence in situ hybridization; ISS = International Staging System

Efficacy was evaluated by ORR as determined by IRC assessment using IMWG criteria. Efficacy results are provided in Table 36. The median DOR was 7.8 months (95% CI: 5.6, 9.2).

Table 36: Response Categories in Study PX-171-003 A1 (20/27 mg/m^2 Monotherapy Regimen)
Characteristics | Study Patients [Eligible patients had 2 or more prior lines of therapy and were refractory to the last regimen.] n (%)
Number of Patients (%) | 266 (100)
Overall Response [As assessed by the Independent Review Committee.] | 61 (23)
95% CI [Exact confidence interval.] | (18, 28)
Response Category
CR | 1 (< 1)
VGPR | 13 (5)
PR | 47 (18)
CI = confidence interval; CR = complete response; PR = partial response; VGPR = very good partial response

Study PX-171-004 Part 2 (NCT00530816)

Study PX-171-004 Part 2 was a single-arm, multicenter clinical trial of Kyprolis monotherapy by up to 10-minute infusion. Eligible patients were those with relapsed or refractory multiple myeloma who were bortezomib-naïve, had received one to three prior lines of therapy and had ≤ 25% response or progression during therapy or within 60 days after completion of therapy. Patients were excluded from the trial if they were refractory to standard first-line therapy or had a total bilirubin ≥ 2 × ULN; creatinine clearance < 30 mL/min; New York Heart Association Class III to IV congestive heart failure; symptomatic cardiac ischemia; myocardial infarction within the last 6 months; active infections requiring treatment; or pleural effusion.

Kyprolis was administered intravenously up to 10 minutes on two consecutive days each week for three weeks, followed by a 12-day rest period (28-day treatment cycle), until disease progression, unacceptable toxicity, or for a maximum of 12 cycles. Patients received 20 mg/m^2 at each dose in Cycle 1, and 27 mg/m^2 in subsequent cycles. Dexamethasone 4 mg orally or intravenously was administered prior to Kyprolis doses in the first and second cycles.

A total of 70 patients were treated with this 20/27 mg/m^2 regimen. Baseline patient and disease characteristics are summarized in Table 37.

Table 37: Demographics and Baseline Characteristics in Study PX-171-004 Part 2 (20/27 mg/m^2 Monotherapy Regimen)
Characteristics | Number of Patients (%)
Patient Characteristics
Enrolled patients | 70 (100)
Median age, years (range) | 66 (45, 85)
Age group, < 65 / ≥ 65 (years) | 31 (44) / 39 (56)
Sex (male / female) | 44 (63) / 26 (37)
Race (White / Black / Asian / Hispanic / Other) | 52 (74) / 12 (17) / 3 (4) / 2 (3) / 1 (1)
Disease Characteristics
Number of Prior Regimens (median) | 2 [Range: 1, 4.]
Prior Transplantation | 47 (67)
Refractory Status to Most Recent Therapy [Categories for refractory status are derived by programmatic assessment using available laboratory data.]
Refractory: Progression during most recent therapy | 28 (40)
Refractory: Progression within 60 days after completion of most recent therapy | 7 (10)
Refractory: ≤ 25% response to treatment | 10 (14)
Relapsed: Progression after 60 days post treatment | 23 (33)
No Signs of Progression | 2 (3)
Years since diagnosis, median (range) | 3.6 (0.7, 12.2)
Plasma cell involvement (< 50% / ≥ 50% / unknown) | 54 (77) / 14 (20) / 1 (1)
ISS Stage at Study Baseline, n (%)
I | 28 (40)
II | 25 (36)
III | 16 (23)
Unknown | 1 (1)
Cytogenetics or FISH analyses
Normal/Favorable | 57 (81)
Poor Prognosis | 10 (14)
Unknown | 3 (4)
Creatinine clearance < 30 mL/min | 1 (1)
FISH = Fluorescence in situ hybridization; ISS = International Staging System

Efficacy was evaluated by ORR as determined by IRC assessment using IMWG criteria. Efficacy results are provided in Table 38. The median DOR was not reached.

Table 38: Response Categories in Study PX-171-004 Part 2 (20/27 mg/m^2 Monotherapy Regimen)
Characteristics | Study Patients [Eligible patients had 1-3 prior lines of therapy and were refractory to the last regimen.] n (%)
Number of Patients (%) | 70 (100)
Overall Response [As assessed by an Independent Review Committee.] | 35 (50)
95% CI [Exact confidence interval.] | (38, 62)
Response Category
CR | 1 (1)
VGPR | 18 (26)
PR | 16 (23)
CI = confidence interval; CR = complete response; PR = partial response; VGPR = very good partial response

16 HOW SUPPLIED/STORAGE AND HANDLING

How Supplied

Kyprolis (carfilzomib) for Injection is supplied as:

- An individually packaged single-dose vial containing 10 mg of carfilzomib as a white to off-white lyophilized cake or powder: NDC 76075-103-01, NDC 76075-103-21.
- An individually packaged single-dose vial containing 30 mg of carfilzomib as a white to off-white lyophilized cake or powder: NDC 76075-102-01, NDC 76075-102-21.
- An individually packaged single-dose vial containing 60 mg of carfilzomib as a white to off-white lyophilized cake or powder: NDC 76075-101-01, NDC 76075-101-21.

Storage and Handling

Unopened vials should be stored refrigerated 2°C to 8°C (36°F to 46°F). Retain in original package to protect from light.

17 PATIENT COUNSELING INFORMATION

Discuss the following with patients prior to treatment with Kyprolis:

Cardiac Toxicities: Advise patients of the risks and symptoms of cardiac failure and ischemia [see Warnings and Precautions (5.1)].

Dehydration: Counsel patients to avoid dehydration, since patients receiving Kyprolis therapy may experience vomiting and/or diarrhea. Instruct patients to seek medical advice if they experience symptoms of dehydration [see Warnings and Precautions (5.3)].

Respiratory: Advise patients that they may experience cough or shortness of breath (dyspnea) during treatment with Kyprolis. This most commonly occurs within a day of dosing. Advise patients to contact their healthcare provider if they experience shortness of breath [see Warnings and Precautions (5.6)].

Venous Thrombosis: Inform patients of the risk of venous thromboembolism and discuss the options for prophylaxis. Advise patients to seek immediate medical attention for symptoms of venous thrombosis or embolism [see Warnings and Precautions (5.8)].

Infusion-Related Reactions: Advise patients of the risk of infusion-related reactions and discuss the common signs and symptoms of infusion-related reactions with the patients [see Warnings and Precautions (5.9)].

Bleeding: Inform patients that they may bruise or bleed more easily or that it may take longer to stop bleeding and to report to their healthcare provider any prolonged, unusual or excessive bleeding. Instruct patients on the signs of occult bleeding [see Warnings and Precautions (5.10)].

Hepatic: Inform patients of the risk of developing hepatic failure. Advise patients to contact their healthcare provider for symptoms of hepatitis including worsening fatigue or yellow discoloration of skin or eyes [see Warnings and Precautions (5.12)].

Other: Inform patients to contact their healthcare provider if they experience neurologic symptoms such as headaches, confusion, dizziness or loss of balance, difficulty talking or walking, decreased strength or weakness on one side of the body, seizures, or visual loss [see Warnings and Precautions (5) and Adverse Reactions (6)].

Driving/Operating Machines: Advise patients that Kyprolis may cause fatigue, dizziness, fainting, and/or drop in blood pressure. Advise patients not to drive or operate machinery if they experience any of these symptoms [see Adverse Reactions (6.1)].

Embryo-Fetal Toxicity: Advise females of the potential risk to the fetus. Advise females of reproductive potential to inform their healthcare provider immediately of a known or suspected pregnancy. Advise female patients to use effective contraceptive during treatment with Kyprolis and for 6 months following the last dose. Advise male patients with female sexual partners of reproductive potential to use effective contraception during treatment with Kyprolis and for 3 months following the last dose [see Warnings and Precautions (5.17), Use in Specific Populations (8.1, 8.3)].

Lactation: Advise patients to avoid breastfeeding while receiving Kyprolis and for 2 weeks after the last dose [see Use in Specific Populations (8.2)].

Concomitant Medications: Advise patients to discuss with their healthcare provider any medication they are currently taking prior to starting treatment with Kyprolis, or prior to starting any new medication(s) during treatment with Kyprolis.

AMGEN®
Kyprolis® (carfilzomib)

Manufactured for:
Onyx Pharmaceuticals, Inc.
One Amgen Center Drive
Thousand Oaks, CA 91320-1799 U.S.A.

Patent: http://pat.amgen.com/kyprolis

©2012-2025 Amgen Inc. All rights reserved.
1XXXXXX V29

PRINCIPAL DISPLAY PANEL

1 Single-Dose Vial
NDC 76075-103-01
AMGEN®
Kyprolis®
(carfilzomib) for Injection
10 mg/vial
10 mg/vial
Single-dose vial. Discard unused portion.
Reconstitution: Reconstitute with 5 mL Sterile Water for Injection, USP.

Dilution: May be further diluted with 5% Dextrose Injection, USP.

For Intravenous Administration Only
Rx Only

PRINCIPAL DISPLAY PANEL

1 Single-Dose Vial

NDC 76075-102-01

AMGEN®

Kyprolis®

(carfilzomib) for Injection

30 mg/vial

30 mg/vial

Single-dose vial. Discard unused portion.

Reconstitution: Reconstitute with 15 mL Sterile Water for Injection, USP.

Dilution: May be further diluted with 5% Dextrose Injection, USP.

For Intravenous Administration Only

Rx Only

PRINCIPAL DISPLAY PANEL

1 Single-Dose Vial

NDC 76075-101-01

AMGEN®

Kyprolis®

(carfilzomib) for Injection

60 mg/vial

60 mg/vial

Single-dose vial. Discard unused portion.

Reconstitution: Reconstitute with 29 mL Sterile Water for Injection, USP.

Dilution: May be further diluted with 5% Dextrose Injection, USP.

For Intravenous Administration Only

Rx Only